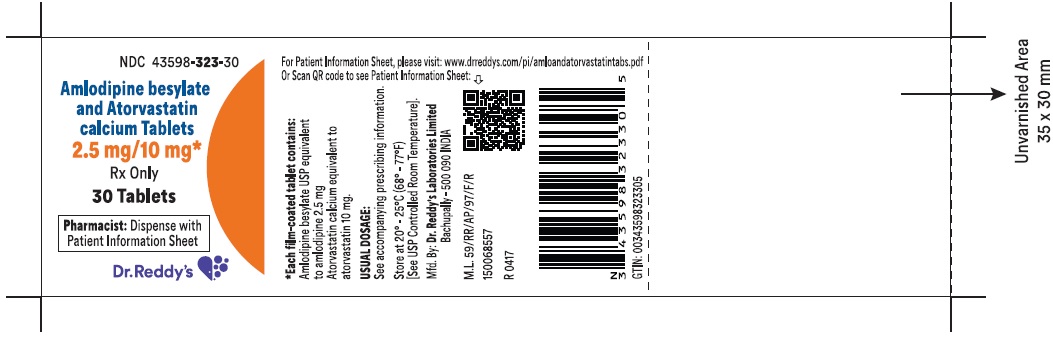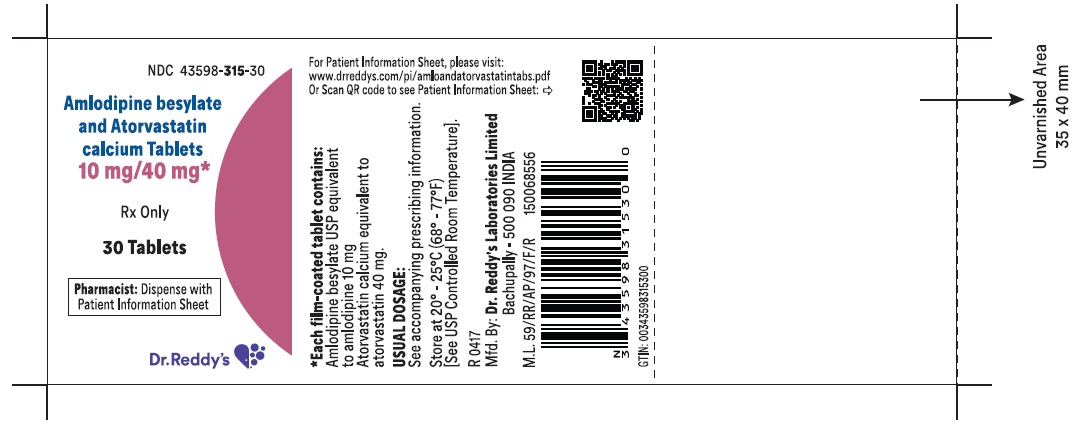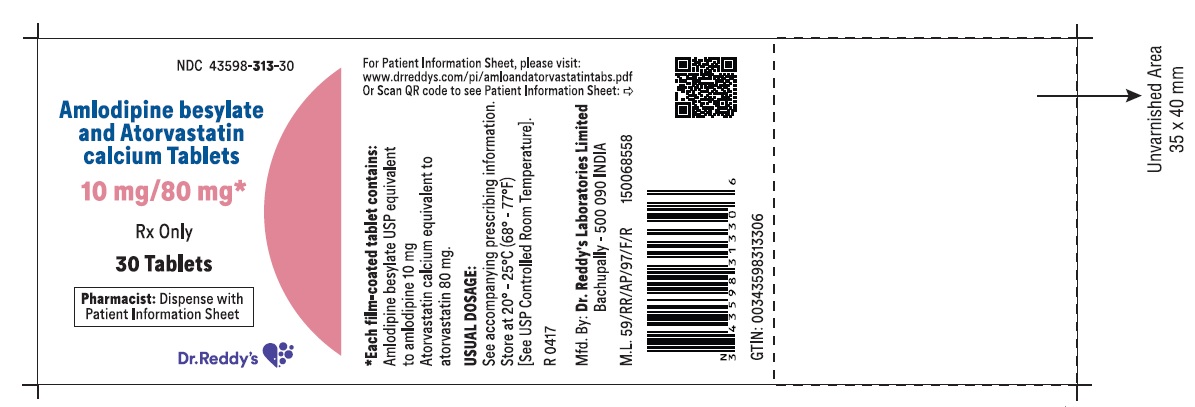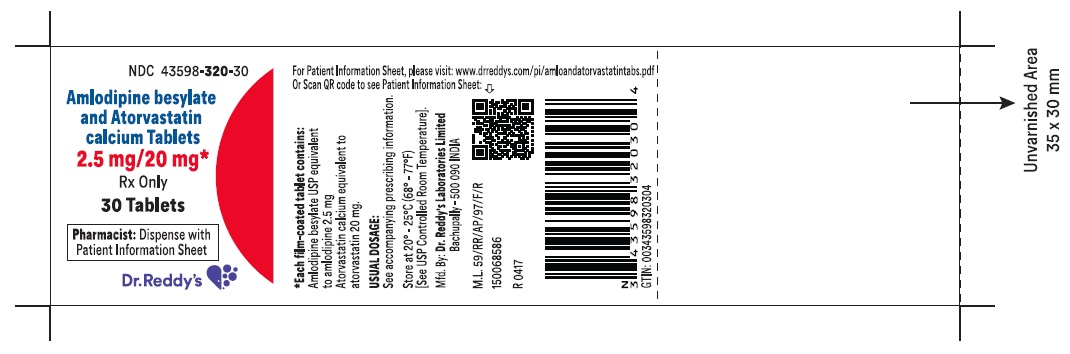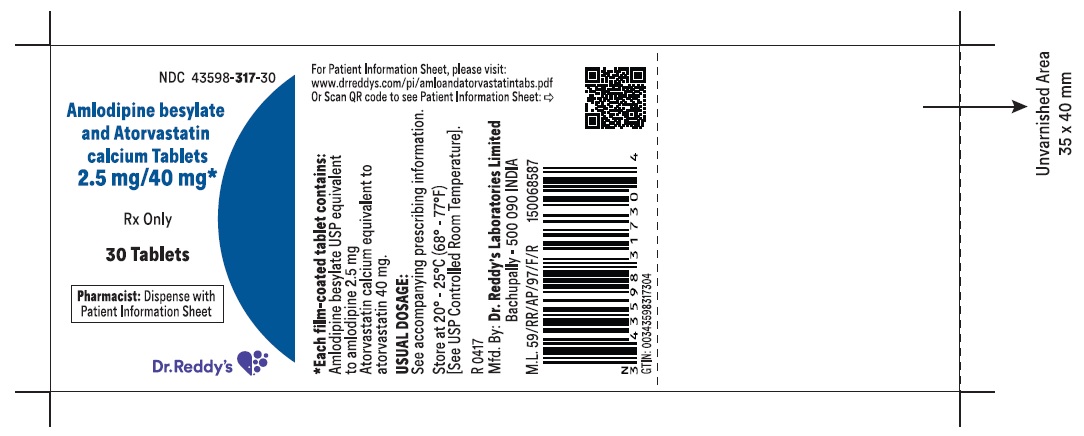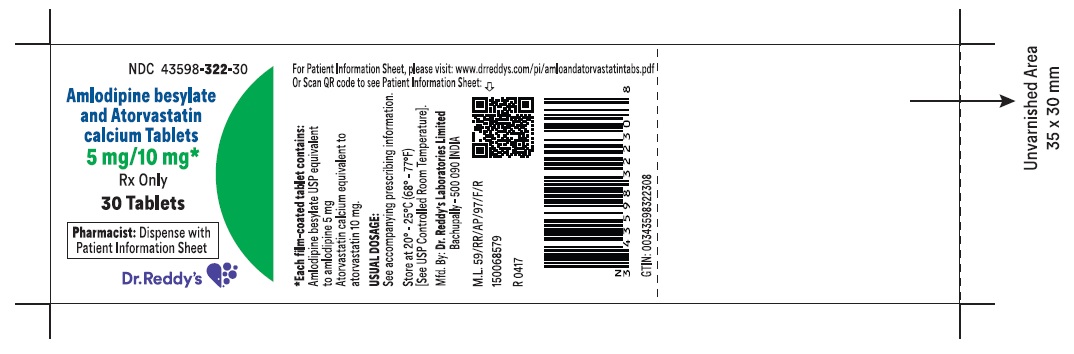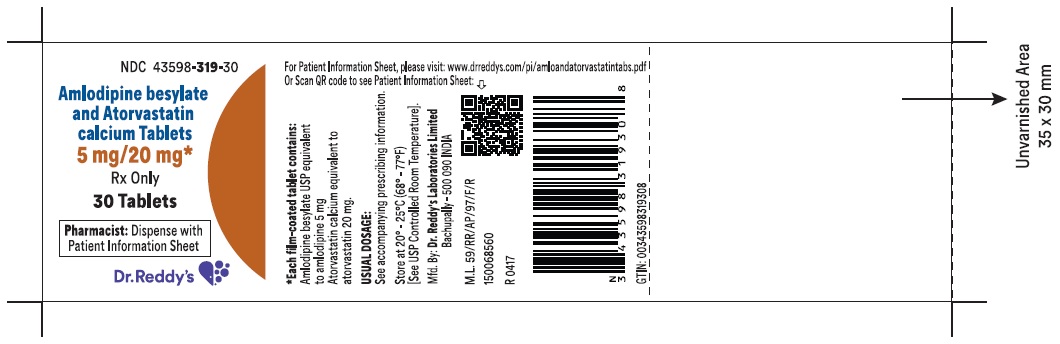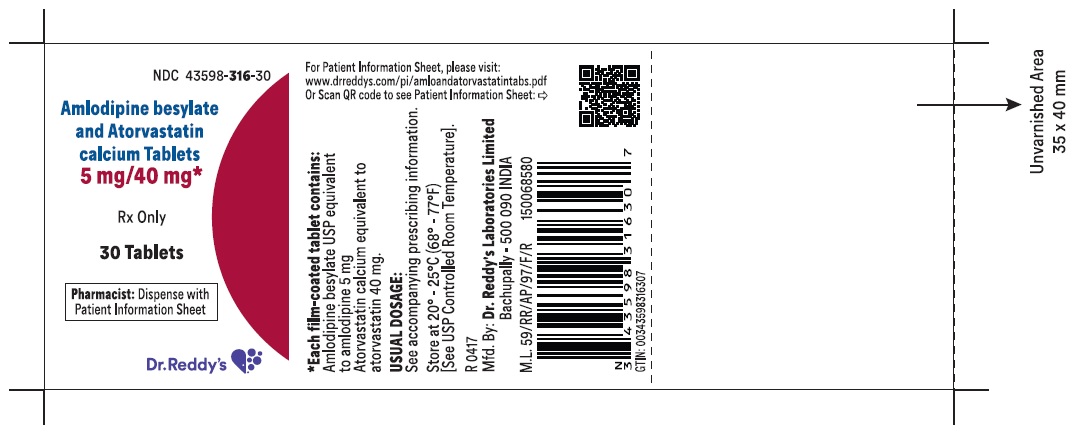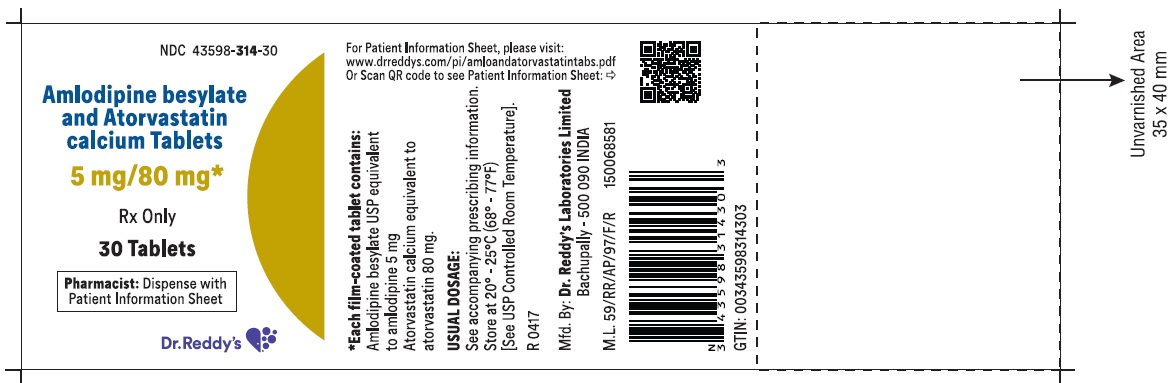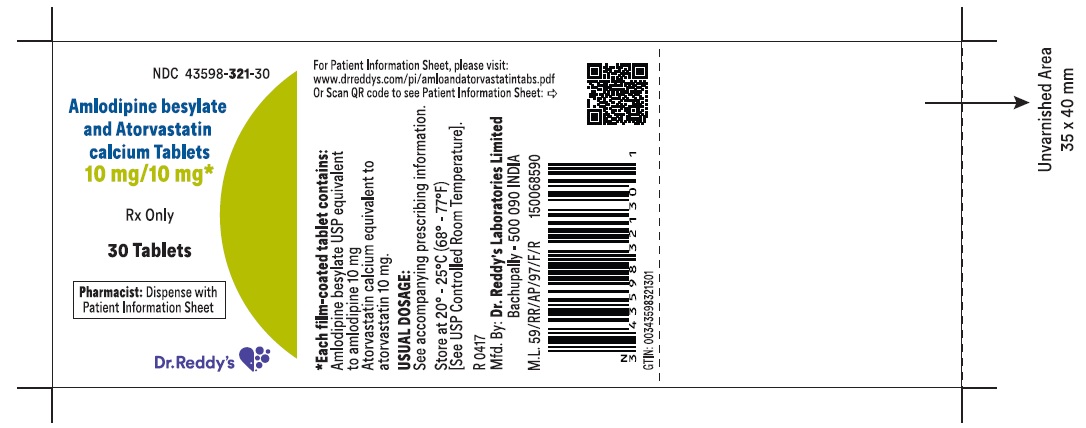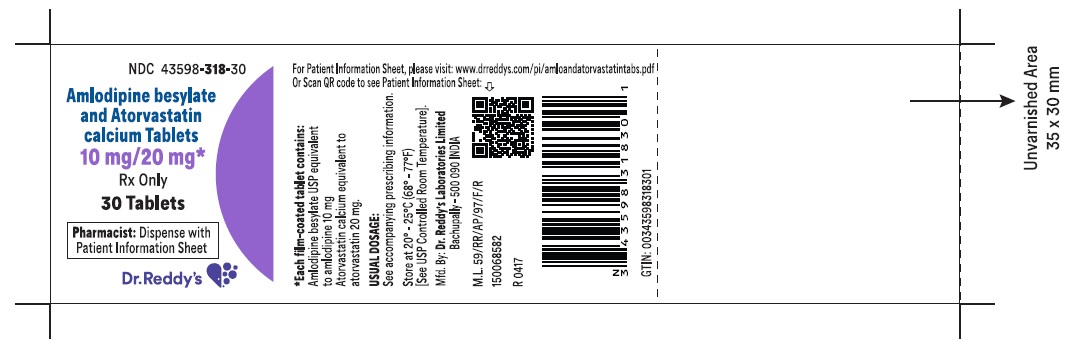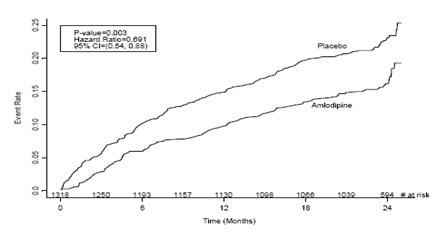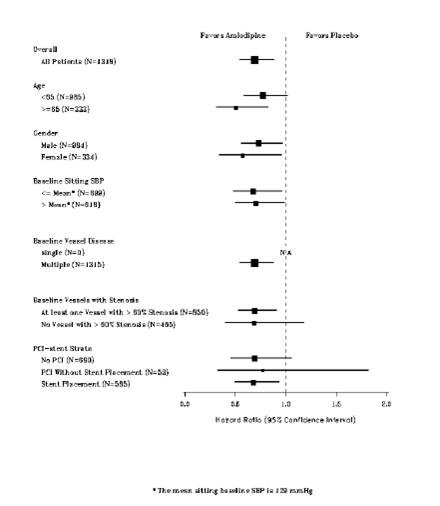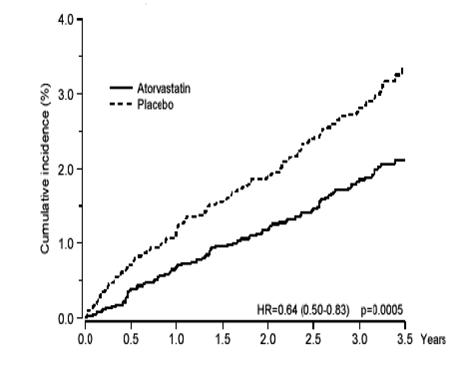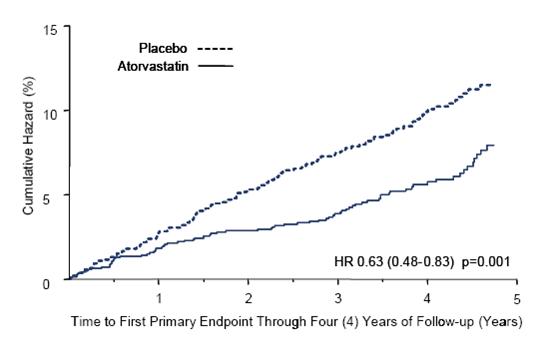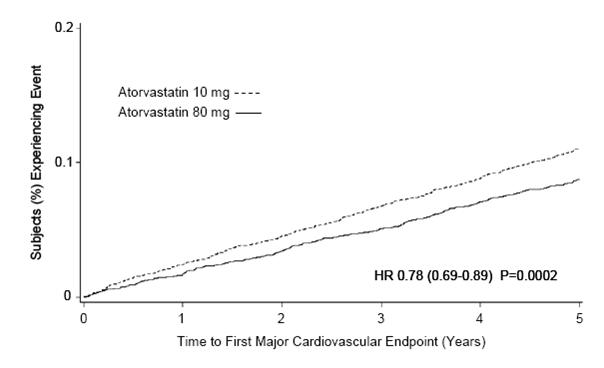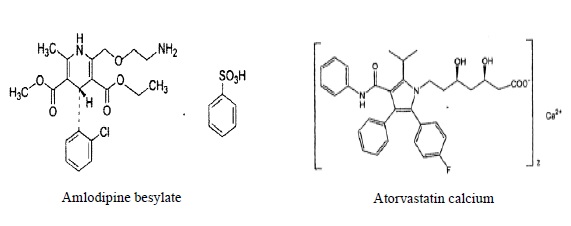 DRUG LABEL: Amlodipine besylate and Atorvastatin calcium
NDC: 43598-323 | Form: TABLET, FILM COATED
Manufacturer: Dr. Reddy's Laboratories Inc
Category: prescription | Type: HUMAN PRESCRIPTION DRUG LABEL
Date: 20210216

ACTIVE INGREDIENTS: amlodipine besylate 2.5 mg/1 1; Atorvastatin Calcium Trihydrate 10 mg/1 1
INACTIVE INGREDIENTS: silicon dioxide; Crospovidone; Hydroxypropyl Cellulose, Unspecified; magnesium stearate; cellulose, microcrystalline; starch, corn; sodium bicarbonate; sodium lauryl sulfate; polyethylene glycol 3350; Polyvinyl Alcohol, Unspecified; Hydrogenated Soybean Lecithin; talc; titanium dioxide

HIGHLIGHTS OF PRESCRIBING INFORMATION

These highlights do not include all the information needed to use AMLODIPINE BESYLATE and ATORVASTATIN CALCIUM TABLETS safely and effectively. See full prescribing information for AMLODIPINE BESYLATE and ATORVASTATIN CALCIUM TABLETS.
AMLODIPINE BESYLATE and ATORVASTATIN CALCIUM tablets, for oral use
Initial U.S. Approval: 2004

RECENT MAJOR CHANGES SECTION

Warnings and Precautions, Myopathy and Rhabdomyolysis (5.1) 01/2021

Warnings and Precautions, Immune-Mediated Necrotizing Myopathy (5.2) 09/2020

1 INDICATIONS AND USAGE

Amlodipine besylate and atorvastatin calcium tablets are a combination of amlodipine besylate, a calcium channel blocker, and atorvastatin calcium, a HMG CoA-reductase inhibitor, indicated in patients for whom treatment with both amlodipine and atorvastatin is appropriate.

Amlodipine is indicated for the treatment of hypertension, to lower blood pressure (1.1). Lowering blood pressure reduces the risk of fatal and nonfatal cardiovascular events, primarily strokes and myocardial infarctions.

Amlodipine is indicated for the treatment of Coronary Artery Disease (1.2).

Atorvastatin is indicated as an adjunct therapy to diet for prevention of cardiovascular disease (1.3) and hyperlipidemia (1.4).

2 DOSAGE AND ADMINISTRATION

 | Usual starting dose (mg daily) | Maximum dose (mg daily)
Amlodipine | 5a | 10
Atorvastatin | 10 to 20b | 80
a Start small adults or children, fragile, or elderly patients, or patients with hepatic insufficiency on 2.5 mg once daily (2)
b Start patients requiring large LDL-C reduction (>45%) at 40 mg once daily (2)

3 DOSAGE FORMS AND STRENGTHS

Tablets contain amlodipine besylate equivalent to amlodipine 2.5, 5, or 10 mg and atorvastatin calcium equivalent to atorvastatin 10, 20, 40, or 80 mg (3).

4 CONTRAINDICATIONS

- Active liver disease (4)
- Pregnancy (4)
- Lactation (4)

5 WARNINGS AND PRECAUTIONS

- Myopathy and Rhabdomyolysis: Advise patients to promptly report to their physician unexplained and/or persistent muscle pain, tenderness, or weakness. Amlodipine besylate and atorvastatin calcium therapy should be discontinued if myopathy is diagnosed or suspected (2, 5.1, 8.5).
- Immune-Mediated Necrotizing Myopathy (IMNM): Monitor for myalgia and treat (5.2).
- Hepatic Transaminitis: Monitor liver enzymes before and during treatment (5.3).
- Symptomatic hypotension is possible, particularly in patients with severe aortic stenosis. However, acute hypotension is unlikely (5.5).
- Angina or myocardial infarction may occur with initiation or dose increase (5.4).

6 ADVERSE REACTIONS

Most common adverse reaction (3% greater than placebo) to amlodipine is edema (6.1).

Most common adverse reactions leading to atorvastatin discontinuation were myalgia and diarrhea (6.1).

To report SUSPECTED ADVERSE REACTIONS, contact Dr. Reddy’s Laboratories, Inc. at 1-888-375-3784 or FDA at 1-800-FDA-1088 or www.fda.gov/medwatch

7 DRUG INTERACTIONS

Increased Risk of Myopathy and Rhabdomyolysis (2, 5.1, 7.3, 12.3)

Cyclosporine, tipranavir plus ritonavir, glecaprevir plus pibrentasvir | Avoid atorvastatin
Clarithromycin, itraconazole, saquinavir plus ritonavir, darunavir plus ritonavir, fosamprenavir, fosamprenavir plus ritonavir, elbasvir plus grazoprevir,letermovir | Do not exceed 20 mg atorvastatin daily
Nelfinavir | Do not exceed 40 mg atorvastatin daily
Lopinavir plus ritonavir, simeprevir, fibric acid derivatives, erythromycin, azole antifungals, lipid-modifying doses of niacin, colchicine | Consider the risk/benefit of concomitant use with atorvastatin

- Other Lipid-Lowering Medications: Increased risk of myopathy (7).
- Rifampin should be simultaneously co-administered with atorvastatin (7.4).
- Oral Contraceptives: Norethindrone and ethinyl estradiol may be increased (7.5).
- Digoxin: Patients should be monitored appropriately (7.5).

8 USE IN SPECIFIC POPULATIONS

- Hepatic Impairment: Plasma concentrations of atorvastatin markedly increased in patients with active liver disease (8.6 ,12.3).
- Females of reproductive potential: Advise females of reproductive potential to use effective contraception during treatment with amlodipine besylate and atorvastatin calcium (8.3).

FULL PRESCRIBING INFORMATION

1 INDICATIONS AND USAGE

Amlodipine besylate and atorvastatin calcium tablets are indicated in patients for whom treatment with both amlodipine and atorvastatin is appropriate.

Amlodipine

1.1 Hypertension

Amlodipine is indicated for the treatment of hypertension, to lower blood pressure. Lowering blood pressure reduces the risk of fatal and nonfatal cardiovascular events, primarily strokes and myocardial infarctions. These benefits have been seen in controlled trials of antihypertensive drugs from a wide variety of pharmacologic classes including amlodipine.

Control of high blood pressure should be part of comprehensive cardiovascular risk management, including, as appropriate, lipid control, diabetes management, antithrombotic therapy, smoking cessation, exercise, and limited sodium intake. Many patients will require more than one drug to achieve blood pressure goals. For specific advice on goals and management, see published guidelines, such as those of the National High Blood Pressure Education Program’s Joint National Committee on Prevention, Detection, Evaluation, and Treatment of High Blood Pressure (JNC).

Numerous antihypertensive drugs, from a variety of pharmacologic classes and with different mechanisms of action, have been shown in randomized controlled trials to reduce cardiovascular morbidity and mortality, and it can be concluded that it is blood pressure reduction, and not some other pharmacologic property of the drugs, that is largely responsible for those benefits. The largest and most consistent cardiovascular outcome benefit has been a reduction in the risk of stroke, but reductions in myocardial infarction and cardiovascular mortality also have been seen regularly.

Elevated systolic or diastolic pressure causes increased cardiovascular risk, and the absolute risk increase per mmHg is greater at higher blood pressures, so that even modest reductions of severe hypertension can provide substantial benefit. Relative risk reduction from blood pressure reduction is similar across populations with varying absolute risk, so the absolute benefit is greater in patients who are at higher risk independent of their hypertension (for example, patients with diabetes or hyperlipidemia), and such patients would be expected to benefit from more aggressive treatment to a lower blood pressure goal.

Some antihypertensive drugs have smaller blood pressure effects (as monotherapy) in black patients, and many antihypertensive drugs have additional approved indications and effects (e.g., on angina, heart failure, or diabetic kidney disease). These considerations may guide selection of therapy.

Amlodipine may be used alone or in combination with other antihypertensive agents.

1.2 Coronary Artery Disease (CAD)

Chronic Stable Angina

Amlodipine is indicated for the symptomatic treatment of chronic stable angina. Amlodipine may be used alone or in combination with other antianginal agents.

Vasospastic Angina (Prinzmetal’s or Variant Angina)

Amlodipine is indicated for the treatment of confirmed or suspected vasospastic angina. Amlodipine may be used as monotherapy or in combination with other antianginal agents.

Angiographically Documented CAD

In patients with recently documented CAD by angiography and without heart failure or an ejection fraction <40%, amlodipine is indicated to reduce the risk of hospitalization for angina and to reduce the risk of a coronary revascularization procedure.

Atorvastatin

Therapy with HMG CoA-reductase inhibitors (lipid-altering agents) should be only one component of multiple risk factor intervention in individuals at significantly increased risk for atherosclerotic vascular disease from hypercholesterolemia. Drug therapy is recommended as an adjunct to diet when the response to a diet restricted in saturated fat and cholesterol and other nonpharmacologic measures alone has been inadequate. In patients with coronary heart disease (CHD) or multiple risk factors for CHD, atorvastatin can be started simultaneously with diet restriction.

1.3 Prevention of Cardiovascular Disease (CVD) in Adults

In adult patients without clinically evident coronary heart disease, but with multiple risk factors for coronary heart disease such as age, smoking, hypertension, low high-density lipoprotein cholesterol (HDL-C), or a family history of early coronary heart disease, atorvastatin is indicated to:

- Reduce the risk of myocardial infarction (MI)
- Reduce the risk of stroke
- Reduce the risk for revascularization procedures and angina

In adult patients with type 2 diabetes, and without clinically evident coronary heart disease, but with multiple risk factors for coronary heart disease such as retinopathy, albuminuria, smoking, or hypertension, atorvastatin is indicated to:

- Reduce the risk of myocardial infarction
- Reduce the risk of stroke

In adult patients with clinically evident coronary heart disease, atorvastatin is indicated to:

- Reduce the risk of non-fatal myocardial infarction
- Reduce the risk of fatal and non-fatal stroke
- Reduce the risk for revascularization procedures
- Reduce the risk of hospitalization for congestive heart failure (CHF)
- Reduce the risk of angina

1.4 Hyperlipidemia

Atorvastatin is indicated:

- As an adjunct to diet to reduce elevated total cholesterol (total-C), low-density lipoprotein cholesterol (LDL-C), apolipoprotein B (apo B), and triglycerides (TG) levels and to increase HDL-C in adult patients with primary hypercholesterolemia (heterozygous familial and nonfamilial) and mixed dyslipidemia (Fredrickson Types IIa and IIb)
- As an adjunct to diet for the treatment of adult patients with elevated serum TG levels (Fredrickson Type IV);
- For the treatment of adult patients with primary dysbetalipoproteinemia (Fredrickson Type III) who do not respond adequately to diet
- To reduce total-C and LDL-C in patients with homozygous familial hypercholesterolemia (HoFH) as an adjunct to other lipid-lowering treatments (e.g., LDL apheresis) or if such treatments are unavailable
- As an adjunct to diet to reduce total-C, LDL-C, and apo B levels in pediatric patients, 10 years to 17 years of age, with heterozygous familial hypercholesterolemia (HeFH) if after an adequate trial of diet therapy the following findings are present:

a. LDL-C remains ≥ 190 mg/dL or

b. LDL-C remains ≥ 160 mg/dL and:

- there is a positive family history of premature CVD or
- two or more other CVD risk factors are present in the pediatric patient

1.5 Limitations of Use

Atorvastatin has not been studied in conditions where the major lipoprotein abnormality is elevation of chylomicrons (Fredrickson Types I and V).

2 DOSAGE AND ADMINISTRATION

Amlodipine besylate and atorvastatin calcium

Dosage of amlodipine besylate and atorvastatin calcium must be individualized on the basis of both effectiveness and tolerance for each individual component in the treatment of hypertension/angina and hyperlipidemia. Select doses of amlodipine and atorvastatin independently.

Amlodipine besylate and atorvastatin calcium may be substituted for its individually titrated components. Patients may be given the equivalent dose of amlodipine besylate and atorvastatin calcium or a dose of amlodipine besylate and atorvastatin calcium with increased amounts of amlodipine, atorvastatin, or both for additional antianginal effects, blood pressure lowering, or lipid-lowering effect.

Amlodipine besylate and atorvastatin calcium may be used to provide additional therapy for patients already on one of its components. Amlodipine besylate and atorvastatin calcium may be used to initiate treatment in patients with hyperlipidemia and either hypertension or angina.

Amlodipine

The usual initial antihypertensive oral dose of amlodipine is 5 mg once daily, and the maximum dose is 10 mg once daily.

Pediatric (age > 6 years), small adult, fragile, or elderly patients, or patients with hepatic insufficiency may be started on 2.5 mg once daily and this dose may be used when adding amlodipine to other antihypertensive therapy.

Adjust dosage according to blood pressure goals. In general, wait 7 to 14 days between titration steps. Titration may proceed more rapidly, however, if clinically warranted, provided the patient is assessed frequently.

Angina: The recommended dose of amlodipine for chronic stable or vasospastic angina is 5 to 10 mg, with the lower dose suggested in the elderly and in patients with hepatic insufficiency. Most patients will require 10 mg for adequate effect.

Coronary Artery Disease: The recommended dose range of amlodipine for patients with CAD is 5 to 10 mg once daily. In clinical studies, the majority of patients required 10 mg [see Clinical Studies (14.4)].

Pediatrics: The effective antihypertensive oral dose of amlodipine in pediatric patients ages 6 to 17 years is 2.5 mg to 5 mg once daily. Doses in excess of 5 mg daily have not been studied in pediatric patients [see Clinical Pharmacology (12.3), Clinical Studies (14.1)].

Atorvastatin (Hyperlipidemia)

Hyperlipidemia and Mixed Dyslipidemia: The recommended starting dose of atorvastatin is 10 or 20 mg once daily. Patients who require a large reduction in LDL-C (more than 45%) may be started at 40 mg once daily. The dosage range of atorvastatin is 10 to 80 mg once daily. Atorvastatin can be administered as a single dose at any time of the day, with or without food. The starting dose and maintenance doses of atorvastatin should be individualized according to patient characteristics such as goal of therapy and response. After initiation and/or upon titration of atorvastatin, lipid levels should be analyzed within 2 to 4 weeks and dosage adjusted accordingly.

Homozygous Familial Hypercholesterolemia: The dosage range of atorvastatin in patients with HoFH is 10 to 80 mg daily. Atorvastatin should be used as an adjunct to other lipid-lowering treatments (e.g., LDL apheresis) in these patients or if such treatments are unavailable.

Concomitant Lipid-Lowering Therapy: Atorvastatin may be used with bile acid resins. Monitor for signs of myopathy in patients receiving the combination of HMG-CoA reductase inhibitors (statins) and fibrates [see Warnings and Precautions (5.1), Drug Interactions (7)].

Patients with Renal Impairment: Renal disease does not affect the plasma concentrations nor LDL-C reduction of atorvastatin; thus, dosage adjustment in patients with renal dysfunction is not necessary [see Warnings and Precautions (5.1), Clinical Pharmacology (12.3)].

Use with Cyclosporine, Clarithromycin, Itraconazole, Letermovir, or Certain Protease Inhibitors: In patients taking cyclosporine or the human immunodeficiency virus (HIV) protease inhibitor tipranavir plus ritonavir or the hepatitis C virus (HCV) protease inhibitor glecaprevir plus pibrentasvir, or letermovir when co-administered with cyclosporine, therapy with atorvastatin should be avoided. In patients with HIV taking lopinavir plus ritonavir, use the lowest dose necessary of atorvastatin. In patients taking clarithromycin, itraconazole, elbasvir plus grazoprevir, or in patients with HIV taking a combination of saquinavir plus ritonavir, darunavir plus ritonavir, fosamprenavir, fosamprenavir plus ritonavir, or letermovir therapy with atorvastatin should be limited to 20 mg, and appropriate clinical assessment is recommended to ensure that the lowest dose necessary of atorvastatin is used. In patients taking the HIV protease inhibitor nelfinavir therapy with atorvastatin should be limited to 40 mg. [see Warnings and Precautions (5.1), Drug Interactions (7.3)].

Heterozygous Familial Hypercholesterolemia in Pediatric Patients (10 Years to 17 Years of Age): The recommended starting dose of atorvastatin is 10 mg/day; the usual dose range is 10 to 20 mg orally once daily [see Clinical Studies (14.11)]. Doses should be individualized according to the recommended goal of therapy [see Indications and Usage (1.4) and Clinical Pharmacology (12)]. Adjustments should be made at intervals of 4 weeks or more.

3 DOSAGE FORMS AND STRENGTHS

Amlodipine besylate and atorvastatin calcium tablets are formulated for oral administration in the following strength combinations:

Amlodipine besylate and atorvastatin calcium tablets 2.5 mg/10 mg are white to off-white, round, film coated tablets debossed ‘R’ on one side and ‘407’ on other side.

Amlodipine besylate and atorvastatin calcium tablets 2.5 mg/20 mg are white to off-white, round, film coated tablets debossed ‘R’ on one side and ‘408’ on other side.

Amlodipine besylate and atorvastatin calcium tablets 2.5 mg/40 mg are white to off-white, round, film coated tablets debossed ‘R’ on one side and ‘409’ on other side.

Amlodipine besylate and atorvastatin calcium tablets 5 mg/10 mg are white to off-white, oval shaped, film coated tablets debossed ‘R’ on one side and ‘410’ on other side.

Amlodipine besylate and atorvastatin calcium tablets 5 mg/20 mg are white to off-white, oval shaped, film coated tablets debossed ‘R’ on one side and ‘411’ on other side.

Amlodipine besylate and atorvastatin calcium tablets 5 mg/40 mg are white to off-white, oval shaped, film coated tablets debossed ‘R’ on one side and ‘412’ on other side.

Amlodipine besylate and atorvastatin calcium tablets 5 mg/80 mg are white to off-white, oval shaped, film coated tablets debossed ‘R’ on one side and ‘413’ on other side.

Amlodipine besylate and atorvastatin calcium tablets 10 mg/10 mg are blue, oval shaped, film coated tablets debossed ‘R’ on one side and ‘414’ on other side.

Amlodipine besylate and atorvastatin calcium tablets 10 mg/20 mg are blue, oval shaped, film coated tablets debossed ‘R’ on one side and ‘415’ on other side.

Amlodipine besylate and atorvastatin calcium tablets 10 mg/40 mg are blue, oval shaped, film coated tablets debossed ‘R’ on one side and ‘416’ on other side.

Amlodipine besylate and atorvastatin calcium tablets 10 mg/80 mg are blue, oval shaped, film coated tablets debossed ‘R’ on one side and ‘417’ on other side.

Combinations of atorvastatin with 2.5 mg and 5 mg amlodipine are film-coated white, and combinations of atorvastatin with 10 mg amlodipine are film-coated blue.

4 CONTRAINDICATIONS

• Active Liver Disease, Which May Include Unexplained Persistent Elevations in Hepatic Transaminase Levels

• Pregnancy [see Use in Specific Populations (8.1)]

• Lactation [see Use in Specific Populations (8.2)]

5 WARNINGS AND PRECAUTIONS

5.1 Myopathy and Rhabdomyolysis

Amlodipine and atorvastatin may cause myopathy (muscle pain, tenderness, or weakness with creatine kinase (CK) above ten times the upper limit of normal) and rhabdomyolysis (with or without acute renal failure secondary to myoglobinuria). Rare fatalities have occurred as a result of rhabdomyolysis with statin use, including amlodipine and atorvastatin.

Risk Factors for Myopathy

Risk factors for myopathy include age 65 years or greater, uncontrolled hypothyroidism, renal impairment, concomitant use with certain other drugs, and higher amlodipine and atorvastatin dosage [see Drug Interactions (7.3)].

Steps to Prevent or Reduce the Risk of Myopathy and Rhabdomyolysis

Amlodipine and atorvastatin exposure may be increased by drug interactions due to inhibition of cytochrome P450 enzyme 3A4 (CYP3A4) and/or transporters (e.g., breast cancer resistant protein [BCRP], organic anion-transporting polypeptide [OATP1B1/OATP1B3] and P-glycoprotein [P-gp]), resulting in an increased risk of myopathy and rhabdomyolysis. Concomitant use of cyclosporine, gemfibrozil, tipranavir plus ritonavir or glecaprevir plus pibrentasvir with amlodipine and atorvastatin is not recommended. Amlodipine and atorvastatin dosage modifications are recommended for patients taking certain anti-viral, azole antifungals, or macrolide antibiotic medications [see Dosage and Administration (2)]. Cases of myopathy/rhabdomyolysis have been reported with atorvastatin co-administered with lipid modifying doses (>1 gram/day) of niacin, fibrates, colchicine, and ledipasvir plus sofosbuvir. Consider if the benefit of use of these products outweighs the increased risk of myopathy and rhabdomyolysis [see Drug Interactions (7.3)].

Concomitant intake of large quantities, more than 1.2 liters daily, of grapefruit juice is not recommended in patients taking amlodipine and atorvastatin tablets[see Drug Interactions (7.3)].

Discontinue amlodipine and atorvastatin tablets if markedly elevated CK levels occur or myopathy is diagnosed or suspected. Muscle symptoms and CK increases may resolve if amlodipine and atorvastatin tablets are discontinued. Temporarily discontinue amlodipine and atorvastatin tablets in patients experiencing an acute or serious condition at high risk of developing renal failure secondary to rhabdomyolysis (e.g., sepsis; shock; severe hypovolemia; major surgery; trauma; severe metabolic, endocrine, or electrolyte disorders; or uncontrolled epilepsy).

Inform patients of the risk of myopathy and rhabdomyolysis when starting or increasing the amlodipine and atorvastatin dosage. Instruct patients to promptly report any unexplained muscle pain, tenderness or weakness, particularly if accompanied by malaise or fever.

5.2 Immune-Mediated Necrotizing Myopathy

There have been rare reports of immune-mediated necrotizing myopathy (IMNM), an autoimmune myopathy, associated with statin use. IMNM is characterized by: proximal muscle weakness and elevated serum creatine kinase, which persist despite discontinuation of statin treatment; positive anti-HMG CoA reductase antibody; muscle biopsy showing necrotizing myopathy; and improvement with immunosuppressive agents. Additional neuromuscular and serologic testing may be necessary. Treatment with immunosuppressive agents may be required. Consider risk of IMNM carefully prior to initiation of a different statin. If therapy is initiated with a different statin, monitor for signs and symptoms of IMNM.

5.3 Liver Dysfunction

Statins, like atorvastatin, and some other lipid-lowering therapies, have been associated with biochemical abnormalities of liver function. Persistent elevations (>3 times the upper limit of normal [ULN] occurring on 2 or more occasions) in serum transaminases occurred in 0.7% of patients who received atorvastatin in clinical trials. The incidence of these abnormalities was 0.2%, 0.2%, 0.6%, and 2.3% for 10, 20, 40, and 80 mg, respectively.

One patient in clinical trials with atorvastatin developed jaundice. Increases in liver function tests (LFT) in other patients were not associated with jaundice or other clinical signs or symptoms. Upon dose reduction, drug interruption, or discontinuation, transaminase levels returned to or near pretreatment levels without sequelae. Eighteen of 30 patients with persistent LFT elevations continued treatment with a reduced dose of atorvastatin.

It is recommended that liver enzyme tests be obtained prior to initiating therapy with atorvastatin and repeated as clinically indicated. There have been rare postmarketing reports of fatal and non-fatal hepatic failure in patients taking statins, including atorvastatin. If serious liver injury with clinical symptoms and/or hyperbilirubinemia or jaundice occurs during treatment with amlodipine besylate and atorvastatin calcium, promptly interrupt therapy. If an alternate etiology is not found, do not restart amlodipine besylate and atorvastatin calcium.

Active liver disease or unexplained persistent transaminase elevations are contraindications to the use of amlodipine besylate and atorvastatin calcium [see Contraindications (4)].

5.4 Increased Angina and Myocardial Infarction

Worsening angina and acute myocardial infarction can develop after starting or increasing the dose of amlodipine, particularly in patients with severe obstructive coronary artery disease.

5.5 Hypotension

Symptomatic hypotension is possible with use of amlodipine, particularly in patients with severe aortic stenosis. Because of the gradual onset of action, acute hypotension is unlikely.

5.6 Endocrine Function

Increases in HbA1c and fasting serum glucose levels have been reported with HMG-CoA reductase inhibitors, including atorvastatin.

Statins interfere with cholesterol synthesis and theoretically might blunt adrenal and/or gonadal steroid production. Clinical studies have shown that atorvastatin does not reduce basal plasma cortisol concentration or impair adrenal reserve. The effects of statins on male fertility have not been studied in adequate numbers of patients. The effects, if any, on the pituitary-gonadal axis in premenopausal women are unknown. Avoid a statin with drugs that may decrease the levels or activity of endogenous steroid hormones such as ketoconazole, spironolactone, and cimetidine.

5.7 CNS Toxicity

Brain hemorrhage was seen in a female dog treated with atorvastatin for 3 months at 120 mg/kg/day. Brain hemorrhage and optic nerve vacuolation were seen in another female dog that was sacrificed in moribund condition after 11 weeks of escalating doses up to 280 mg/kg/day. The 120 mg/kg dose resulted in a systemic exposure approximately 16 times the human plasma area-under-the-curve (AUC, 0-24 hours) based on the maximum human dose of 80 mg/day. A single tonic convulsion was seen in each of 2 male dogs (one treated at 10 mg/kg/day and one at 120 mg/kg/day) in a 2-year study. No CNS lesions have been observed in mice after chronic treatment for up to 2 years at doses up to 400 mg/kg/day or in rats at doses up to 100 mg/kg/day. These doses were 6 to 11 times (mouse) and 8 to 16 times (rat) the human AUC (0-24) based on the maximum recommended human dose (MRHD) of 80 mg/day.

CNS vascular lesions, characterized by perivascular hemorrhages, edema, and mononuclear cell infiltration of perivascular spaces, have been observed in dogs treated with other statins. A chemically similar drug in this class produced optic nerve degeneration (Wallerian degeneration of retinogeniculate fibers) in clinically normal dogs in a dose-dependent fashion at a dose that produced plasma drug levels about 30 times higher than the mean drug level in humans taking the highest recommended dose.

5.8 Hemorrhagic Stroke

In a post-hoc analysis of the Stroke Prevention by Aggressive Reduction in Cholesterol Levels (SPARCL) study where atorvastatin 80 mg vs. placebo was administered in 4,731 subjects without CHD who had a stroke or TIA within the preceding 6 months, a higher incidence of hemorrhagic stroke was seen in the atorvastatin 80 mg group compared to placebo (55, 2.3% atorvastatin vs. 33, 1.4% placebo; HR: 1.68, 95% CI: 1.09, 2.59; p=0.0168). The incidence of fatal hemorrhagic stroke was similar across treatment groups (17 vs. 18 for the atorvastatin and placebo groups, respectively). The incidence of non-fatal hemorrhagic stroke was significantly higher in the atorvastatin group (38, 1.6%) as compared to the placebo group (16, 0.7%). Some baseline characteristics, including hemorrhagic and lacunar stroke on study entry, were associated with a higher incidence of hemorrhagic stroke in the atorvastatin group [see Adverse Reactions (6.1)].

6 ADVERSE REACTIONS

The following serious adverse reactions are discussed in greater detail in other sections of the label:

- Myopathy and Rhabdomyolysis [see Warnings and Precautions (5.1)]
- Liver enzyme abnormalities [see Warnings and Precautions (5.3)]

6.1 Clinical Trials Experience

Because clinical trials are conducted under widely varying conditions, adverse reaction rates observed in the clinical trials of a drug cannot be directly compared to rates in the clinical trials of another drug and may not reflect the rates observed in practice.

Amlodipine besylate and atorvastatin calcium

Amlodipine besylate and atorvastatin calcium has been evaluated for safety in 1,092 patients in double-blind placebo-controlled studies treated for co-morbid hypertension and dyslipidemia. In general, treatment with amlodipine besylate and atorvastatin calcium was well tolerated. For the most part, adverse reactions have been mild or moderate in severity. In clinical trials with amlodipine besylate and atorvastatin calcium, no adverse reactions peculiar to this combination have been observed. Adverse reactions are similar in terms of nature, severity, and frequency to those reported previously with amlodipine and atorvastatin.

The following information is based on the clinical experience with amlodipine and atorvastatin.

Amlodipine

Amlodipine has been evaluated for safety in more than 11,000 patients in U.S. and foreign clinical trials. In general, treatment with amlodipine was well tolerated at doses up to 10 mg daily. Most adverse reactions reported during therapy with amlodipine were of mild or moderate severity. In controlled clinical trials directly comparing amlodipine (N=1,730) at doses up to 10 mg to placebo (N=1,250), discontinuation of amlodipine because of adverse reactions was required in only about 1.5% of patients and was not significantly different from placebo (about 1%). The most commonly reported side effects more frequent than placebo are dizziness and edema. The incidence (%) of side effects that occurred in a dose-related manner are as follows:

 | 2.5 mg N=275 | Amlodipine 5 mg N=296 | 10 mg N=268 | Placebo N=520
Edema | 1.8 | 3 | 10.8 | 0.6
Dizziness | 1.1 | 3.4 | 3.4 | 1.5
Flushing | 0.7 | 1.4 | 2.6 | 0
Palpitations | 0.7 | 1.4 | 4.5 | 0.6

Other adverse reactions that were not clearly dose related but were reported at an incidence greater than 1% in placebo-controlled clinical trials include the following:

 | Amlodipine (%) (N=1730) | Placebo (%) (N=1250)
Fatigue | 4.5 | 2.8
Nausea | 2.9 | 1.9
Abdominal Pain | 1.6 | 0.3
Somnolence | 1.4 | 0.6

Edema, flushing, palpitations, and somnolence appear to be more common in women than in men.

The following events occurred in <1% but >0.1% of patients treated with amlodipine in controlled clinical trials or under conditions of open trials or marketing experience where a causal relationship is uncertain; they are listed to alert the physician to a possible relationship:

Cardiovascular: arrhythmia (including ventricular tachycardia and atrial fibrillation), bradycardia, chest pain, peripheral ischemia, syncope, tachycardia, vasculitis.

Central and Peripheral Nervous System: hypoesthesia, neuropathy peripheral, paresthesia, tremor, vertigo.

Gastrointestinal: anorexia, constipation, dysphagia, diarrhea, flatulence, pancreatitis, vomiting, gingival hyperplasia.

General: allergic reaction, asthenia,^2 back pain, hot flushes, malaise, pain, rigors, weight gain, weight decrease.

Musculoskeletal System: arthralgia, arthrosis, muscle cramps,^2 myalgia.

Psychiatric: sexual dysfunction (male^2 and female), insomnia, nervousness, depression, abnormal dreams, anxiety, depersonalization.

Respiratory System: dyspnea,^2 epistaxis.

Skin and Appendages: angioedema, erythema multiforme, pruritus,^2 rash,^2 rash erythematous, rash maculopapular.

Special Senses: abnormal vision, conjunctivitis, diplopia, eye pain, tinnitus.

Urinary System: micturition frequency, micturition disorder, nocturia.

Autonomic Nervous System: dry mouth, sweating increased.

Metabolic and Nutritional: hyperglycemia, thirst.

Hemopoietic: leukopenia, purpura, thrombocytopenia.

^2 These events occurred in less than 1% in placebo-controlled trials, but the incidence of these side effects was between 1% and 2% in all multiple dose studies.

Amlodipine therapy has not been associated with clinically significant changes in routine laboratory tests. No clinically relevant changes were noted in serum potassium, serum glucose, total TG, TC, HDL-C, uric acid, blood urea nitrogen, or creatinine.

Atorvastatin

In the atorvastatin placebo-controlled clinical trial database of 16,066 patients (8,755 atorvastatin vs. 7,311 placebo; age range 10 to 93 years, 39% women, 91% Caucasians, 3% Blacks, 2% Asians, 4% other) with a median treatment duration of 53 weeks, 9.7% of patients on atorvastatin and 9.5% of the patients on placebo discontinued because of adverse reactions regardless of causality. The five most common adverse reactions in patients treated with atorvastatin that led to treatment discontinuation and occurred at a rate greater than placebo were: myalgia (0.7%), diarrhea (0.5%), nausea (0.4%), alanine aminotransferase increase (0.4%), and hepatic enzyme increase (0.4%).

The most commonly reported adverse reactions (incidence ≥ 2% and greater than placebo) regardless of causality, in patients treated with atorvastatin in placebo-controlled trials (n=8,755) were: nasopharyngitis (8.3%), arthralgia (6.9%), diarrhea (6.8%), pain in extremity (6%), and urinary tract infection (5.7%).

Table 2 summarizes the frequency of clinical adverse reactions, regardless of causality, reported in ≥ 2% and at a rate greater than placebo in patients treated with atorvastatin (n=8,755), from seventeen placebo-controlled trials.

Table 2. Clinical Adverse Reactions Occurring in ≥ 2% in Patients Treated with Any Dose of Atorvastatin and at an Incidence Greater than Placebo Regardless of Causality (% of Patients)
Adverse Reaction* | Any dose N=8755 | 10 mg N=3908 | 20 mg N=188 | 40 mg N=604 | 80 mg N=4055 | Placebo N=7311
Nasopharyngitis | 8.3 | 12.9 | 5.3 | 7 | 4.2 | 8.2
Arthralgia | 6.9 | 8.9 | 11.7 | 10.6 | 4.3 | 6.5
Diarrhea | 6.8 | 7.3 | 6.4 | 14.1 | 5.2 | 6.3
Pain in extremity | 6 | 8.5 | 3.7 | 9.3 | 3.1 | 5.9
Urinary tract infection | 5.7 | 6.9 | 6.4 | 8 | 4.1 | 5.6
Dyspepsia | 4.7 | 5.9 | 3.2 | 6 | 3.3 | 4.3
Nausea | 4 | 3.7 | 3.7 | 7.1 | 3.8 | 3.5
Musculoskeletal pain | 3.8 | 5.2 | 3.2 | 5.1 | 2.3 | 3.6
Muscle spasms | 3.6 | 4.6 | 4.8 | 5.1 | 2.4 | 3
Myalgia | 3.5 | 3.6 | 5.9 | 8.4 | 2.7 | 3.1
Insomnia | 3 | 2.8 | 1.1 | 5.3 | 2.8 | 2.9
Pharyngolaryngeal pain | 2.3 | 3.9 | 1.6 | 2.8 | 0.7 | 2.1
* Adverse Reaction ≥2% in any dose greater than placebo.

Other adverse reactions reported in placebo-controlled studies include:

Body as a whole: malaise, pyrexia; Digestive system: abdominal discomfort, eructation, flatulence, hepatitis, cholestasis; Musculoskeletal system: musculoskeletal pain, muscle fatigue, neck pain, joint swelling; Metabolic and nutritional system: transaminases increase, liver function test abnormal, blood alkaline phosphatase increase, creatine phosphokinase increase, hyperglycemia; Nervous system: nightmare; Respiratory system: epistaxis; Skin and appendages: urticaria; Special senses: vision blurred, tinnitus; Urogenital system: white blood cells urine positive.

Treating to New Targets Study (TNT)

In TNT [see Clinical Studies (14.6)] involving 10,001 subjects (age range 29 to 78 years, 19% women; 94.1% Caucasians, 2.9% Blacks, 1% Asians, 2% other) with clinically evident CHD treated with atorvastatin 10 mg daily (n=5,006) or atorvastatin 80 mg daily (n=4,995), serious adverse reactions and discontinuations because of adverse reactions increased with dose. Persistent transaminase elevations (≥3 x ULN twice within 4 to 10 days) occurred in 62 (1.3%) individuals with atorvastatin 80 mg and in nine (0.2%) individuals with atorvastatin 10 mg. Elevations of CK (≥ 10 x ULN) were low overall, but were higher in the high-dose atorvastatin treatment group (13, 0.3%) compared to the low-dose atorvastatin group (6, 0.1%).

Stroke Prevention by Aggressive Reduction in Cholesterol Levels (SPARCL)

In SPARCL involving 4,731 subjects (age range 21 to 92 years, 40% women; 93.3% Caucasians, 3% Blacks, 0.6% Asians, 3.1% other) without clinically evident CHD but with a stroke or transient ischemic attack (TIA) within the previous 6 months treated with atorvastatin 80 mg (n=2,365) or placebo (n=2,366) for a median follow-up of 4.9 years, there was a higher incidence of persistent hepatic transaminase elevations (≥ 3 x ULN twice within 4 to 10 days) in the atorvastatin group (0.9%) compared to placebo (0.1%). Elevations of CK (>10 x ULN) were rare, but were higher in the atorvastatin group (0.1%) compared to placebo (0%). Diabetes was reported as an adverse reaction in 144 subjects (6.1%) in the atorvastatin group and 89 subjects (3.8%) in the placebo group [see Warnings and Precautions (5.6)].

In a post-hoc analysis, atorvastatin 80 mg reduced the incidence of ischemic stroke (218/2365, 9.2% vs. 274/2366, 11.6%) and increased the incidence of hemorrhagic stroke (55/2365, 2.3% vs. 33/2366, 1.4%) compared to placebo. The incidence of fatal hemorrhagic stroke was similar between groups (17 atorvastatin vs. 18 placebo). The incidence of non-fatal hemorrhagic strokes was significantly greater in the atorvastatin group (38 non-fatal hemorrhagic strokes) as compared to the placebo group (16 non-fatal hemorrhagic strokes). Subjects who entered the study with a hemorrhagic stroke appeared to be at increased risk for hemorrhagic stroke [7 (16%) atorvastatin vs. 2 (4%) placebo].

There were no significant differences between the treatment groups for all-cause mortality: 216 (9.1%) in the atorvastatin 80 mg/day group vs. 211 (8.9%) in the placebo group. The proportions of subjects who experienced cardiovascular death were numerically smaller in the atorvastatin 80 mg group (3.3%) than in the placebo group (4.1%). The proportions of subjects who experienced non-cardiovascular death were numerically larger in the atorvastatin 80 mg group (5%) than in the placebo group (4%).

Adverse Reactions from Clinical Studies of Atorvastatin in Pediatric Patients

In a 26-week controlled study in boys and postmenarchal girls with HeFH (ages 10 years to 17 years) (n=140, 31% female; 92% Caucasians, 1.6% Blacks, 1.6% Asians, 4.8% Other), the safety and tolerability profile of atorvastatin 10 to 20 mg daily, as an adjunct to diet to reduce TC, LDL-C, and apo B levels, was generally similar to that of placebo [see Use in Specific Populations (8.4) and Clinical Studies (14.11)].

6.2 Postmarketing Experience

The following adverse reactions have been identified during post-approval of amlodipine and atorvastatin. Because these reactions are reported voluntarily from a population of uncertain size, it is not always possible to reliably estimate their frequency or establish a causal relationship to drug exposure.

Amlodipine

The following postmarketing event has been reported infrequently where a causal relationship is uncertain: gynecomastia. In postmarketing experience, jaundice and hepatic enzyme elevations (mostly consistent with cholestasis or hepatitis), in some cases severe enough to require hospitalization, have been reported in association with use of amlodipine.

Postmarketing reporting has also revealed a possible association between extrapyramidal disorder and amlodipine.

Amlodipine has been used safely in patients with chronic obstructive pulmonary disease, well-compensated congestive heart failure, coronary artery disease, peripheral vascular disease, diabetes mellitus, and abnormal lipid profiles.

Atorvastatin

Adverse reactions associated with atorvastatin therapy reported since market introduction that are not listed above, regardless of causality assessment, include the following: anaphylaxis, angioneurotic edema, bullous rashes (including erythema multiforme, Stevens-Johnson syndrome, and toxic epidermal necrolysis), rhabdomyolysis, myositis, fatigue, tendon rupture, fatal and non-fatal hepatic failure, dizziness, depression, peripheral neuropathy, pancreatitis and interstitial lung disease.

There have been rare reports of immune-mediated necrotizing myopathy associated with statin use [see Warnings and Precautions (5.2)].

There have been rare postmarketing reports of cognitive impairment (e.g., memory loss, forgetfulness, amnesia, memory impairment, confusion) associated with statin use. These cognitive issues have been reported for all statins. The reports are generally nonserious, and reversible upon statin discontinuation, with variable times to symptom onset (1 day to years) and symptom resolution (median of 3 weeks).

7 DRUG INTERACTIONS

Data from a drug-drug interaction study involving 10 mg of amlodipine and 80 mg of atorvastatin in healthy subjects indicate that the pharmacokinetics of amlodipine are not altered when the drugs are co-administered. The effect of amlodipine on the pharmacokinetics of atorvastatin showed no effect on the Cmax: 91% (90% confidence interval: 80 to 103%), but the AUC of atorvastatin increased by 18% (90% confidence interval: 109 to 127%) in the presence of amlodipine, which is not clinically meaningful.

No drug interaction studies have been conducted with amlodipine besylate and atorvastatin calcium and other drugs, although studies have been conducted in the individual amlodipine and atorvastatin components, as described below:

Amlodipine

7.1 Impact of Other Drugs on Amlodipine

CYP3A Inhibitors

Co-administration with CYP3A inhibitors (moderate and strong) results in increased systemic exposure to amlodipine and may require dose reduction. Monitor for symptoms of hypotension and edema when amlodipine is co-administered with CYP3A inhibitors to determine the need for dose adjustment [see Clinical Pharmacology (12.3)].

CYP3A Inducers

No information is available on the quantitative effects of CYP3A inducers on amlodipine. Blood pressure should be closely monitored when amlodipine is co-administered with CYP3A inducers.

Sildenafil

Monitor for hypotension when sildenafil is co-administered with amlodipine [see Clinical Pharmacology (12.2)].

7.2 Impact of Amlodipine on Other Drugs

Immunosuppressants

Amlodipine may increase the systemic exposure of cyclosporine or tacrolimus when co-administered. Frequent monitoring of trough blood levels of cyclosporine and tacrolimus is recommended and adjust the dose when appropriate [see Clinical Pharmacology (12.3)].

Atorvastatin

The risk of myopathy during treatment with statins is increased with concurrent administration of fibric acid derivatives, lipid-modifying doses of niacin, cyclosporine, or strong CYP3A4 inhibitors (e.g., clarithromycin, HIV and HCV protease inhibitors, and itraconazole) [see Warnings and Precautions (5.1) and Clinical Pharmacology (12.3)].

7.3 Drug Interactions that may Increase the Risk of Myopathy and Rhabdomyolysis with Atorvastatin

Atorvastatin is a substrate of CYP3A4 and transporters (e.g., OATP1B1/1B3, P-gp, or BCRP). Atorvastatin plasma levels can be significantly increased with concomitant administration of inhibitors of CYP3A4 and transporters. Table 3 includes a list of drugs that may increase exposure to atorvastatin and may increase the risk of myopathy and rhabdomyolysis when used concomitantly and instructions for preventing or managing them [see Warnings and Precautions (5.1) and Clinical Pharmacology (12.3)].

Table 3: Drug Interactions that may Increase the Risk of Myopathy and Rhabdomyolysis with Atorvastatin

Cyclosporine or Gemfibrozil
Clinical Impact: | Atorvastatin plasma levels were significantly increased with concomitant administration of atorvastatin and cyclosporine, an inhibitor of CYP3A4 and OATP1B1 [see Clinical Pharmacology (12.3)]. Gemfibrozil may cause myopathy when given alone. The risk of myopathy and rhabdomyolysis is increased with concomitant use of cyclosporine or gemfibrozil with atorvastatin.
Intervention: | Concomitant use of cyclosporine or gemfibrozil with atorvastatin calcium is not recommended
Anti-Viral Medications
Clinical Impact: | Atorvastatin plasma levels were significantly increased with concomitant administration of atorvastatin with many anti-viral medications, which are inhibitors of CYP3A4 and/or transporters (e.g., BCRP, OATP1B1/1B3, P-gp, MRP2, and/or OAT2) [see Clinical Pharmacology (12.3)]. Cases of myopathy and rhabdomyolysis have been reported with concomitant use of ledipasvir plus sofosbuvir with atorvastatin.
Intervention: | - Concomitant use of tipranavir plus ritonavir or glecaprevir plus pibrentasvir with atorvastatin is not recommended. - In patients taking lopinavir plus ritonavir, or simeprevir, consider the risk/benefit of concomitant use with atorvastatin. - In patients taking saquinavir plus ritonavir, darunavir plus ritonavir, fosamprenavir,fosamprenavir plus ritonavir, elbasvir plus grazoprevir or letermovir, do not exceed atorvastatin 20 mg. - In patients taking nelfinavir, do not exceed atorvastatin 40 mg [see Dosage and Administration (2)].Consider the risk/benefit of concomitant use of ledipasvir plus sofosbuvir with atorvastatin. - Monitor all patients for signs and symptoms of myopathy particularly during initiation of therapy and during upward dose titration of either drug.
Examples: | Tipranavir plus ritonavir, glecaprevir plus pibrentasvir, lopinavir plus ritonavir, simeprevir, saquinavir plus ritonavir, darunavir plus ritonavir, fosamprenavir, fosamprenavir plus ritonavir, elbasvir plus grazoprevir, letermovir, nelfinavir, and ledipasvir plus sofosbuvir.
Select Azole Antifungals or Macrolide Antibiotics
Clinical Impact: | Atorvastatin plasma levels were significantly increased with concomitant administration of atorvastatin with select azole antifungals or macrolide antibiotics, due to inhibition of CYP3A4 and/or transporters [see Clinical Pharmacology (12.3)].
Intervention: | In patients taking clarithromycin or itraconazole, do not exceed atorvastatin 20 mg [see Dosage and Administration (2)]. Consider the risk/benefit of concomitant use of other azole antifungals or macrolide antibiotics with atorvastatin. Monitor all patients for signs and symptoms of myopathy particularly during initiation of therapy and during upward dose titration of either drug.
Examples: | Erythromycin, clarithromycin, itraconazole, ketoconazole, posaconazole, and voriconazole.
Niacin
Clinical Impact: | Cases of myopathy and rhabdomyolysis have been observed with concomitant use of lipid modifying dosages of niacin (>1 gram/day niacin) with atorvastatin.
Intervention: | Consider if the benefit of using lipid modifying dosages of niacin concomitantly with atorvastatin outweighs the increased risk of myopathy and rhabdomyolysis. If concomitant use is decided, monitor patients for signs and symptoms of myopathy particularly during initiation of therapy and during upward dose titration of either drug.
Fibrates (other than Gemfibrozil)
Clinical Impact: | Fibrates may cause myopathy when given alone. The risk of myopathy and rhabdomyolysis is increased with concomitant use of fibrates with atorvastatin.
Intervention: | Consider if the benefit of using fibrates concomitantly with atorvastatin outweighs the increased risk of myopathy and rhabdomyolysis. If concomitant use is decided, monitor patients for signs and symptoms of myopathy particularly during initiation of therapy and during upward dose titration of either drug.
Colchicine
Clinical Impact: | Cases of myopathy and rhabdomyolysis have been reported with concomitant use of colchicine with atorvastatin.
Intervention: | Consider the risk/benefit of concomitant use of colchicine with atorvastatin. If concomitant use is decided, monitor patients for signs and symptoms of myopathy particularly during initiation of therapy and during upward dose titration of either drug.
Grapefruit Juice
Clinical Impact: | Grapefruit juice consumption, especially excessive consumption, more than 1.2 liters/daily, can raise the plasma levels of atorvastatin and may increase the risk of myopathy and rhabdomyolysis.
Intervention: | Avoid intake of large quantities of grapefruit juice, more than 1.2 liters daily, when taking atorvastatin.

7.4 Drug Interactions that may Decrease Exposure to Atorvastatin

Table 4 presents drug interactions that may decrease exposure to atorvastatin and instructions for preventing or managing them.

Table 4: Drug Interactions that may Decrease Exposure to Atorvastatin

Rifampin
Clinical Impact: | Concomitant administration of atorvastatin with rifampin, an inducer of cytochrome P450 3A4 and inhibitor of OATP1B1, can lead to variable reductions in plasma concentrations of atorvastatin. Due to the dual interaction mechanism of rifampin, delayed administration of atorvastatin after administration of rifampin has been associated with a significant reduction in atorvastatin plasma concentrations.
Intervention: | Administer atorvastatin and rifampin simultaneously.

7.5 Atorvastatin Effects on Other Drugs

Table 5 presents atorvastatin effect on other drugs and instructions for preventing or managing them.

Table 5: Atorvastatin Effects on Other Drugs

Oral Contraceptives
Clinical Impact: | Co-administration of atorvastatin and an oral contraceptive increased plasma concentrations of norethindrone and ethinyl estradiol [see Clinical Pharmacology (12.3)].
Intervention: | Consider this when selecting an oral contraceptive for patients taking atorvastatin.
Digoxin
Clinical Impact: | When multiple doses of atorvastatin and digoxin were co-administered, steady state plasma digoxin concentrations increased [see Clinical Pharmacology (12.3)].
Intervention: | Monitor patients taking digoxin appropriately.

8 USE IN SPECIFIC POPULATIONS

8.1 Pregnancy

Risk Summary

Amlodipine besylate and atorvastatin calcium tablets are contraindicated in women who are pregnant.

Atorvastatin

Atorvastatin is contraindicated for use in pregnant women since safety in pregnant women has not been established and there is no apparent benefit of lipid lowering drugs during pregnancy. Because HMG-CoA reductase inhibitors decrease cholesterol synthesis and possibly the synthesis of other biologically active substances derived from cholesterol, atorvastatin may cause fetal harm when administered to a pregnant woman. Amlodipine besylate and atorvastatin calcium tablets should be discontinued as soon as pregnancy is recognized [see Contraindications (4)]. Limited published data on the use of atorvastatin are insufficient to determine a drug-associated risk of major congenital malformations or miscarriage. In animal reproduction studies in rats and rabbits there was no evidence of embryo-fetal toxicity or congenital malformations at doses up to 30 and 20 times, respectively, the human exposure at the MRHD of 80 mg, based on body surface area (mg/m^2). In rats administered atorvastatin during gestation and lactation, decreased postnatal growth and development was observed at doses ≥6 times the MRHD (see Data).

Amlodipine

The limited available data based on post-marketing reports with amlodipine use in pregnant women are not sufficient to inform a drug-associated risk for major birth defects and miscarriage. There are risks to the mother and fetus associated with poorly controlled hypertension in pregnancy (see Clinical Considerations). In animal reproduction studies, there was no evidence of adverse developmental effects when pregnant rats and rabbits were treated orally with amlodipine maleate during organogenesis at doses approximately 10 and 20 times MRHD, respectively. However for rats, litter size was significantly decreased (by about 50%) and the number of intrauterine deaths was significantly increased (about 5-fold). Amlodipine has been shown to prolong both the gestation period and the duration of labor in rats at this dose (see Data).

The estimated background risk of major birth defects and miscarriage for the indicated population is unknown. All pregnancies have a background risk of birth defect, loss or other adverse outcomes. In the U.S. general population, the estimated background risk of major birth defects and miscarriage in clinically recognized pregnancies is 2 to 4% and 15 to 20%, respectively.

Clinical Considerations

Disease-associated maternal and/or embryo/fetal risk

Hypertension in pregnancy increases the maternal risk for pre-eclampsia, gestational diabetes, premature delivery, and delivery complications (e.g., need for cesarean section and post-partum hemorrhage). Hypertension increases the fetal risk for intrauterine growth restriction and intrauterine death. Pregnant women with hypertension should be carefully monitored and managed accordingly.

Data

Human Data

Atorvastatin

Limited published data on atorvastatin calcium from observational studies, meta-analyses and case reports have not shown an increased risk of major congenital malformations or miscarriage. Rare reports of congenital anomalies have been received following intrauterine exposure to other HMG-CoA reductase inhibitors. In a review of approximately 100 prospectively followed pregnancies in women exposed to simvastatin or lovastatin, the incidences of congenital anomalies, spontaneous abortions, and fetal deaths/stillbirths did not exceed what would be expected in the general population. The number of cases is adequate to exclude a ≥3 to 4-fold increase in congenital anomalies over the background incidence. In 89% of the prospectively followed pregnancies, drug treatment was initiated prior to pregnancy and was discontinued at some point in the first trimester when pregnancy was identified.

Animal Data

Atorvastatin

Atorvastatin crosses the rat placenta and reaches a level in fetal liver equivalent to that of maternal plasma. When administered to pregnant rats and rabbits during organogenesis at oral doses up to 300 mg/kg/day and 100 mg/kg/day, respectively, atorvastatin was not teratogenic in rats at doses up to 300 mg/kg/day or in rabbits at doses up to 100 mg/kg/day. These doses resulted in multiples of about 30 times (rat) or 20 times (rabbit) the human exposure at the MRHD based on surface area (mg/m^2). In rats, the maternally toxic dose of 300 mg/kg resulted in increased post-implantation loss and decreased fetal body weight. At the maternally toxic doses of 50 and 100 mg/kg/day in rabbits, there was increased post-implantation loss, and at 100 mg/kg/day fetal body weights were decreased.

In a study in pregnant rats administered atorvastatin calcium at doses equivalent to 20, 100, or 225 mg/kg/day, from gestation day 7 through to lactation day 20 (weaning), there was decreased survival at birth, postnatal day 4, weaning, and post-weaning in pups of mothers dosed with 225 mg/kg/day, a dose at which maternal toxicity was observed. Pup body weight was decreased through postnatal day 21 at 100 mg/kg/day, and through postnatal day 91 at 225 mg/kg/day. Pup development was delayed (rotorod performance at 100 mg/kg/day and acoustic startle at 225 mg/kg/day; pinnae detachment and eye-opening at 225 mg/kg/day). These doses of atorvastatin correspond to 6 times (100 mg/kg) and 22 times (225 mg/kg) the human exposure at the MRHD, based on AUC.

Amlodipine

No evidence of teratogenicity or other embryo/fetal toxicity was found when pregnant rats and rabbits were treated orally with amlodipine maleate at doses up to 10 mg amlodipine/kg/day (approximately 10 and 20 times the MRHD based on body surface area, respectively) during their respective periods of major organogenesis. However, for rats, litter size was significantly decreased (by about 50%) and the number of intrauterine deaths was significantly increased (about 5-fold) in rats receiving amlodipine maleate at a dose equivalent to 10 mg amlodipine/kg/day for 14 days before mating and throughout mating and gestation. Amlodipine maleate has been shown to prolong both the gestation period and the duration of labor in rats at this dose.

8.2 Lactation

Risk Summary

Amlodipine besylate and atorvastatin calcium tablets are contraindicated during breastfeeding.

Atorvastatin

Atorvastatin use is contraindicated during breastfeeding [see Contraindications (4)]. There is no available information on the effects of the drug on the breastfed infant or the effects of the drug on milk production. It is not known whether atorvastatin is present in human milk, but it has been shown that another drug in this class passes into human milk and atorvastatin is present in rat milk. Because of the potential for serious adverse reactions in a breastfed infant, advise women that breastfeeding is not recommended during treatment with amlodipine besylate and atorvastatin calcium.

Amlodipine

Limited available data from a published clinical lactation study reports that amlodipine is present in human milk at an estimated median relative infant dose of 4.2%. No adverse effects of amlodipine on the breastfed infant have been observed. There is no available information on the effects of amlodipine on milk production.

8.3 Females and Males of Reproductive Potential

Contraception

Atorvastatin may cause fetal harm when administered to a pregnant woman. Advise females of reproductive potential to use effective contraception during treatment with amlodipine besylate and atorvastatin calcium [see Use in Specific Populations (8.1)].

8.4 Pediatric Use

The safety and effectiveness of amlodipine besylate and atorvastatin calcium have not been established in pediatric populations.

Amlodipine

Amlodipine (2.5 to 5 mg daily) is effective in lowering blood pressure in patients 6 to 17 years [see Clinical Studies (14.1)]. The effect of amlodipine on blood pressure in patients less than 6 years of age is not known.

Atorvastatin

Heterozygous Familial Hypercholesterolemia (HeFH)

Safety and effectiveness of atorvastatin have been established in patients 10 years to 17 years of age with HeFH as an adjunct to diet to reduce total cholesterol, LDL-C, and apo B levels when, after an adequate trial of diet therapy, the following are present:

• LDL-C ≥190 mg/dL, or

• LDL-C ≥160 mg/dL and

- a positive family history of FH, or premature CVD in a first, or second-degree relative, or
- two or more other CVD risk factors are present.

Use of atorvastatin for this indication is supported by evidence from [see Dosage and Administration (2), Adverse Reactions (6.1), Clinical Pharmacology (12.3), and Clinical Studies (14.11)]:

• A placebo-controlled clinical trial of 6 months duration in 187 boys and postmenarchal girls, 10 years to 17 years of age. Patients treated with 10 mg or 20 mg daily atorvastatin had an adverse reaction profile generally similar to that of patients treated with placebo. In this limited controlled study, there was no significant effect on growth or sexual maturation in boys or on menstrual cycle length in girls

• A three year open-label uncontrolled trial that included 163 pediatric patients 10 to 15 years of age with HeFH who were titrated to achieve a target LDL-C <130 mg/dL. The safety and efficacy of atorvastatin in lowering LDL-C appeared generally consistent with that observed for adult patients, despite limitations of the uncontrolled study design.

Advise postmenarchal girls of contraception recommendations, if appropriate for the patient [see Use in Specific Populations (8.1)].

The long-term efficacy of atorvastatin therapy initiated in childhood to reduce morbidity and mortality in adulthood has not been established.

The safety and efficacy of atorvastatin have not been established in pediatric patients younger than 10 years of age with HeFH.

Homozygous Familial Hypercholesterolemia (HoFH)

Clinical efficacy of atorvastatin with dosages up to 80 mg/day for 1 year was evaluated in an uncontrolled study of patients with HoFH including 8 pediatric patients [see Clinical Studies (14.10)].

8.5 Geriatric Use

Safety and effectiveness of amlodipine besylate and atorvastatin calcium have not been established in geriatric populations.

Amlodipine

Clinical studies of amlodipine did not include sufficient numbers of subjects aged 65 and over to determine whether they respond differently from younger subjects. Other reported clinical experience has not identified differences in responses between the elderly and younger patients. In general, dose selection for an elderly patient should be cautious, usually starting at the low end of the dosing range, reflecting the greater frequency of decreased hepatic, renal, or cardiac function, and of concomitant disease or other drug therapy. Elderly patients have decreased clearance of amlodipine with a resulting increase of AUC of approximately 40 to 60%, and a lower initial dose may be required [see Dosage and Administration (2)].

Atorvastatin

Of the 39,828 patients who received atorvastatin in clinical studies, 15,813 (40%) were ≥65 years old and 2,800 (7%) were ≥75 years old. No overall differences in safety or effectiveness were observed between these subjects and younger subjects, and other reported clinical experience has not identified differences in responses between the elderly and younger patients, but greater sensitivity of some older adults cannot be ruled out. Advanced age (≥65 years) is a predisposing factor for myopathy.

8.6 Hepatic Impairment

Amlodipine besylate and atorvastatin calcium is contraindicated in patients with active liver disease which may include unexplained persistent elevations in hepatic transaminase levels [see Contraindications (4) and Clinical Pharmacology (12.3)].

10 OVERDOSAGE

There is no information on overdosage with amlodipine besylate and atorvastatin calcium in humans.

Amlodipine

Overdosage might be expected to cause excessive peripheral vasodilation with marked hypotension and possibly a reflex tachycardia. In humans, experience with intentional overdosage of amlodipine is limited.

Single oral doses of amlodipine maleate equivalent to 40 mg amlodipine/kg and 100 mg amlodipine/kg in mice and rats, respectively, caused deaths. Single oral amlodipine maleate doses equivalent to 4 or more mg amlodipine/kg or higher in dogs (11 or more times the MRHD on a mg/m^2 basis) caused a marked peripheral vasodilation and hypotension.

If overdose should occur with amlodipine, initiate active cardiac and respiratory monitoring. Perform frequent blood pressure measurements. Should hypotension occur,provide cardiovascular support including elevation of the extremities and administration of fluids. If hypotension remains unresponsive to these conservative measures, consider administration of vasopressors (such as phenylephrine) with specific attention to circulating volume and urine output. As amlodipine is highly protein bound, hemodialysis is not likely to be of benefit.

Atorvastatin

There is no specific treatment for atorvastatin overdosage. In the event of an overdose, the patient should be treated symptomatically, and supportive measures instituted as required. Because of extensive drug binding to plasma proteins, hemodialysis is not expected to significantly enhance atorvastatin clearance.

11 DESCRIPTION

Amlodipine besylate and atorvastatin calcium tablets combine the calcium channel blocker amlodipine besylate USP with the HMG CoA-reductase inhibitor atorvastatin calcium.

The amlodipine besylate USP is chemically described as 3-ethyl-5-methyl (4RS)-2-[(2-aminoethoxy)methyl]-4-(2-chlorophenyl)-6-methyl-1,4-dihydropyridine-3,5-dicarboxylate benzenesulphonate. Its molecular formula is C20H25ClN2O5•C6H6O3S.

The atorvastatin calcium is chemically described as [R-(R*, R*)]-2-(4-fluorophenyl)-ß, δ-dihydroxy-5-(1-methylethyl)-3-phenyl-4-[(phenylamino)carbonyl]-1H-pyrrole-1-heptanoic acid, calcium salt (2:1). Its molecular formula is C66H68CaF2N4O10.

The structural formulae for amlodipine besylate USP and atorvastatin calcium are shown below.

Amlodipine besylate and atorvastatin calcium contains amlodipine besylate USP, a white or almost white powder, and atorvastatin calcium, a white to off-white colored powder, free from visible extraneous matter. Amlodipine besylate USP has a molecular weight of 567.1 and atorvastatin calcium has a molecular weight of 1155.36. Amlodipine besylate USP is freely soluble in methanol, sparingly soluble in ethanol, slightly soluble in water and in 2-proponal. Atorvastatin calcium is soluble in dimethyl sulphoxide, slightly soluble in alcohol, very slightly soluble in water, in pH 7.4 phosphate buffer and in acetonitrile and practically insoluble in aqueous solutions of pH 4 and below.

Amlodipine besylate and atorvastatin calcium is available as film-coated tablets containing:

- 2.5 mg amlodipine equivalent to 3.468 mg amlodipine besylate USP and 10 mg atorvastatin equivalent to 10.341 mg atorvastatin calcium.
- 2.5 mg amlodipine equivalent to 3.468 mg amlodipine besylate USP and 20 mg atorvastatin equivalent to 20.683 mg atorvastatin calcium.
- 2.5 mg amlodipine equivalent to 3.468 mg amlodipine besylate USP and 40 mg atorvastatin equivalent to 41.365 mg atorvastatin calcium.
- 5 mg amlodipine equivalent to 6.935 mg amlodipine besylate USP and 10 mg atorvastatin equivalent to 10.341 mg atorvastatin calcium.
- 5 mg amlodipine equivalent to 6.935 mg amlodipine besylate USP and 20 mg atorvastatin equivalent to 20.683 mg atorvastatin calcium.
- 5 mg amlodipine equivalent to 6.935 mg amlodipine besylate USP and 40 mg atorvastatin equivalent to 41.365 mg atorvastatin calcium.
- 5 mg amlodipine equivalent to 6.935 mg amlodipine besylate USP and 80 mg atorvastatin equivalent to 82.730 mg atorvastatin calcium.
- 10 mg amlodipine equivalent to 13.870 mg amlodipine besylate USP and 10 mg atorvastatin equivalent to 10.341 mg atorvastatin calcium.
- 10 mg amlodipine equivalent to 13.870 mg amlodipine besylate USP and 20 mg atorvastatin equivalent to 20.683 mg atorvastatin calcium.
- 10 mg amlodipine equivalent to 13.870 mg amlodipine besylate USP and 40 mg atorvastatin equivalent to 41.365 mg atorvastatin calcium.
- 10 mg amlodipine equivalent to 13.870 mg amlodipine besylate USP and 80 mg atorvastatin equivalent to 82.730 mg atorvastatin calcium.

Each film-coated tablet also contains colloidal silicon dioxide, crospovidone, hydroxy propyl cellulose, magnesium stearate, microcrystalline cellulose, pregelatinized starch, sodium bicarbonate, sodium lauryl sulfate, Opadry- II White 85G18490 (Polyethylene glycol, polyvinyl alcohol, lecithin, talc and titanium dioxide), or Opadry- II Blue 85G50642 (FD&C Blue No.2, polyethylene glycol, polyvinyl alcohol, lecithin, talc and titanium dioxide).

12 CLINICAL PHARMACOLOGY

12.1 Mechanism of Action

Amlodipine besylate and atorvastatin calcium is a combination of two drugs, a dihydropyridine calcium channel blocker (amlodipine) and an HMG-CoA reductase inhibitor (atorvastatin). The amlodipine component of amlodipine besylate and atorvastatin calcium inhibits the transmembrane influx of calcium ions into vascular smooth muscle and cardiac muscle. The atorvastatin component of amlodipine besylate and atorvastatin calcium is a selective, competitive inhibitor of HMG-CoA reductase, the rate-limiting enzyme that converts 3-hydroxy-3-methylglutaryl-coenzyme A to mevalonate, a precursor of sterols, including cholesterol.

Amlodipine

Amlodipine binds to both dihydropyridine and nondihydropyridine binding sites. The contractile processes of cardiac muscle and vascular smooth muscle are dependent upon the movement of extracellular calcium ions into these cells through specific ion channels. Amlodipine inhibits calcium ion influx across cell membranes selectively, with a greater effect on vascular smooth muscle cells than on cardiac muscle cells. Negative inotropic effects can be detected in vitro but such effects have not been seen in intact animals at therapeutic doses. Serum calcium concentration is not affected by amlodipine.

Amlodipine is a peripheral arterial vasodilator that acts directly on vascular smooth muscle to cause a reduction in peripheral vascular resistance and reduction in blood pressure. The precise mechanisms by which amlodipine relieves angina have not been fully delineated, but are thought to include the following:

Exertional Angina: In patients with exertional angina, amlodipine reduces the total peripheral resistance (afterload) against which the heart works and reduces the rate pressure product, and thus myocardial oxygen demand, at any given level of exercise.

Vasospastic Angina: Amlodipine has been demonstrated to block constriction and restore blood flow in coronary arteries and arterioles in response to calcium, potassium epinephrine, serotonin, and thromboxane A2 analog in experimental animal models and in human coronary vessels in vitro. This inhibition of coronary spasm is responsible for the effectiveness of amlodipine in vasospastic (Prinzmetal’s or variant) angina.

Atorvastatin

Atorvastatin is a selective, competitive inhibitor of HMG-CoA reductase, the rate-limiting enzyme that converts 3-hydroxy-3-methylglutaryl-coenzyme A to mevalonate, a precursor of sterols, including cholesterol. In animal models, atorvastatin lowers plasma cholesterol and lipoprotein levels by inhibiting HMG-CoA reductase and cholesterol synthesis in the liver and by increasing the number of hepatic LDL receptors on the cell surface to enhance uptake and catabolism of LDL; atorvastatin also reduces LDL production and the number of LDL particles.

12.2 Pharmacodynamics

Amlodipine

Following administration of therapeutic doses to patients with hypertension, amlodipine produces vasodilation resulting in a reduction of supine and standing blood pressures. These decreases in blood pressure are not accompanied by a significant change in heart rate or plasma catecholamine levels with chronic dosing. Although the acute intravenous administration of amlodipine decreases arterial blood pressure and increases heart rate in hemodynamic studies of patients with chronic stable angina, chronic oral administration of amlodipine in clinical trials did not lead to clinically significant changes in heart rate or blood pressures in normotensive patients with angina.

With chronic once daily oral administration, antihypertensive effectiveness is maintained for at least 24 hours. Plasma concentrations correlate with effect in both young and elderly patients. The magnitude of reduction in blood pressure with amlodipine is also correlated with the height of pretreatment elevation; thus, individuals with moderate hypertension (diastolic pressure 105 to 114 mmHg) had about a 50% greater response than patients with mild hypertension (diastolic pressure 90 to 104 mmHg). Normotensive subjects experienced no clinically significant change in blood pressures (+1/–2 mmHg).

In hypertensive patients with normal renal function, therapeutic doses of amlodipine resulted in a decrease in renal vascular resistance and an increase in glomerular filtration rate and effective renal plasma flow without change in filtration fraction or proteinuria.

As with other calcium channel blockers, hemodynamic measurements of cardiac function at rest and during exercise (or pacing) in patients with normal ventricular function treated with amlodipine have generally demonstrated a small increase in cardiac index without significant influence on dP/dt or on left ventricular end diastolic pressure or volume. In hemodynamic studies, amlodipine has not been associated with a negative inotropic effect when administered in the therapeutic dose range to intact animals and man, even when co-administered with beta-blockers to man. Similar findings, however, have been observed in normal or well-compensated patients with heart failure with agents possessing significant negative inotropic effects.

Amlodipine does not change sinoatrial nodal function or atrioventricular conduction in intact animals or man. In patients with chronic stable angina, intravenous administration of 10 mg did not significantly alter A-H and H-V conduction and sinus node recovery time after pacing. Similar results were obtained in patients receiving amlodipine and concomitant beta-blockers. In clinical studies in which amlodipine was administered in combination with beta-blockers to patients with either hypertension or angina, no adverse effects on electrocardiographic parameters were observed. In clinical trials with angina patients alone, amlodipine therapy did not alter electrocardiographic intervals or produce higher degrees of AV blocks.

Atorvastatin

Atorvastatin, as well as some of its metabolites, are pharmacologically active in humans. The liver is the primary site of action and the principal site of cholesterol synthesis and LDL clearance. Drug dosage, rather than systemic drug concentration, correlates better with LDL-C reduction. Individualization of drug dosage should be based on therapeutic response [see Dosage and Administration (2)].

Drug interactions

Sildenafil: When amlodipine and sildenafil were used in combination, each agent independently exerted its own blood pressure lowering effect [see Drug Interactions (7.1)].

12.3 Pharmacokinetics

Absorption

Amlodipine: After oral administration of therapeutic doses of amlodipine alone, absorption produces peak plasma concentrations between 6 and 12 hours. Absolute bioavailability has been estimated to be between 64% and 90%.

Atorvastatin: After oral administration alone, atorvastatin is rapidly absorbed; maximum plasma concentrations occur within 1 to 2 hours. Extent of absorption increases in proportion to atorvastatin dose. The absolute bioavailability of atorvastatin (parent drug) is approximately 14% and the systemic availability of HMG-CoA reductase inhibitory activity is approximately 30%. The low systemic availability is attributed to presystemic clearance in gastrointestinal mucosa and/or hepatic first-pass metabolism. Plasma atorvastatin concentrations are lower (approximately 30% for Cmax and AUC) following evening drug administration compared with morning. However, LDL-C reduction is the same regardless of the time of day of drug administration [see Dosage and Administration (2)].

Amlodipine besylate and atorvastatin calcium: Following oral administration of amlodipine besylate and atorvastatin calcium, peak plasma concentrations of amlodipine and atorvastatin are seen at 6 to 12 hours and 1 to 2 hours post dosing, respectively. The rate and extent of absorption (bioavailability) of amlodipine and atorvastatin from amlodipine besylate and atorvastatin calcium are not significantly different from the bioavailability of amlodipine and atorvastatin administered separately (see above).

The bioavailability of amlodipine from amlodipine besylate and atorvastatin calcium was not affected by food. Food decreases the rate and extent of absorption of atorvastatin from amlodipine besylate and atorvastatin calcium by approximately 32% and 11%, respectively, as it does with atorvastatin when given alone. LDL-C reduction is similar whether atorvastatin is given with or without food.

Distribution

Amlodipine: Ex vivo studies have shown that approximately 93% of the circulating amlodipine drug is bound to plasma proteins in hypertensive patients. Steady-state plasma levels of amlodipine are reached after 7 to 8 days of consecutive daily dosing.

Atorvastatin: Mean volume of distribution of atorvastatin is approximately 381 liters. Atorvastatin is ≥98% bound to plasma proteins. A blood/plasma ratio of approximately 0.25 indicates poor drug penetration into red blood cells. Based on observations in rats, atorvastatin calcium is likely to be secreted in human milk [see Contraindications (4) and Use in Specific Populations (8.3)].

Metabolism

Amlodipine: Amlodipine is extensively (about 90%) converted to inactive metabolites via hepatic metabolism.

Atorvastatin: Atorvastatin is extensively metabolized to ortho- and parahydroxylated derivatives and various beta-oxidation products. In vitro inhibition of HMG-CoA reductase by ortho- and parahydroxylated metabolites is equivalent to that of atorvastatin. Approximately 70% of circulating inhibitory activity for HMG-CoA reductase is attributed to active metabolites. In vitro studies suggest the importance of atorvastatin metabolism by cytochrome P4503A4, consistent with increased plasma concentrations of atorvastatin in humans following co-administration with erythromycin, a known inhibitor of this isozyme [see Drug Interactions (7)]. In animals, the ortho-hydroxy metabolite undergoes further glucuronidation.

Excretion

Amlodipine: Elimination from the plasma is biphasic with a terminal elimination half-life of about 30 to 50 hours. Ten percent of the parent amlodipine compound and 60% of the metabolites of amlodipine are excreted in the urine.

Atorvastatin: Atorvastatin and its metabolites are eliminated primarily in bile following hepatic and/or extra-hepatic metabolism; however, the drug does not appear to undergo enterohepatic recirculation. Mean plasma elimination half-life of atorvastatin in humans is approximately 14 hours, but the half-life of inhibitory activity for HMG-CoA reductase is 20 to 30 hours because of the contribution of active metabolites. Less than 2% of a dose of atorvastatin is recovered in urine following oral administration.

Specific Populations

Geriatric

Amlodipine: Elderly patients have decreased clearance of amlodipine with a resulting increase in AUC of approximately 40 to 60%, and a lower initial dose of amlodipine may be required.

Atorvastatin: Plasma concentrations of atorvastatin are higher (approximately 40% for Cmax and 30% for AUC) in healthy elderly subjects (age ≥65 years) than in young adults. Clinical data suggest a greater degree of LDL-lowering at any dose of atorvastatin in the elderly population compared to younger adults [see Use in Specific Populations (8.5)].

Pediatric

Amlodipine: Sixty-two hypertensive patients aged 6 to 17 years received doses of amlodipine between 1.25 mg and 20 mg. Weight-adjusted clearance and volume of distribution were similar to values in adults.

Atorvastatin: Apparent oral clearance of atorvastatin in pediatric subjects appeared similar to that of adults when scaled allometrically by body weight as the body weight was the only significant covariate in atorvastatin population pharmacokinetics model with data including pediatric HeFH patients (ages 10 years to 17 years of age, n=29) in an open-label, 8-week study.

Gender

Atorvastatin: Plasma concentrations of atorvastatin in women differ from those in men (approximately 20% higher for Cmax and 10% lower for AUC); however, there is no clinically significant difference in LDL-C reduction with atorvastatin between men and women.

Renal Impairment

Amlodipine: The pharmacokinetics of amlodipine are not significantly influenced by renal impairment. Patients with renal failure may therefore receive the usual initial amlodipine dose.

Atorvastatin: Renal disease has no influence on the plasma concentrations or LDL-C reduction of atorvastatin; thus, dose adjustment of atorvastatin in patients with renal dysfunction is not necessary [see Dosage and Administration (2) and Warnings and Precautions (5.1)].

Hemodialysis

While studies have not been conducted in patients with end-stage renal disease, hemodialysis is not expected to clear atorvastatin or amlodipine since both drugs are extensively bound to plasma proteins.

Hepatic Impairment

Amlodipine: Elderly patients and patients with hepatic insufficiency have decreased clearance of amlodipine with a resulting increase in AUC of approximately 40 to 60%.

Atorvastatin: In patients with chronic alcoholic liver disease, plasma concentrations of atorvastatin are markedly increased. Cmax and AUC are each 4-fold greater in patients with Childs-Pugh A disease. Cmax and AUC of atorvastatin are approximately 16-fold and 11-fold increased, respectively, in patients with Childs-Pugh B disease [see Contraindications (4)].

Atorvastatin is contraindicated in patients with active liver disease.

Heart Failure

Amlodipine: In patients with moderate to severe heart failure, the increase in AUC for amlodipine was similar to that seen in the elderly and in patients with hepatic insufficiency.

Effects of Other Drugs on Amlodipine besylate and atorvastatin calcium

Amlodipine:

Co-administered cimetidine, magnesium-and aluminum hydroxide antacids, sildenafil, and grapefruit juice have no impact on the exposure to amlodipine.

CYP3A inhibitors: Co-administration of a 180 mg daily dose of diltiazem with 5 mg amlodipine in elderly hypertensive patients resulted in a 60% increase in amlodipine systemic exposure. Erythromycin co-administration in healthy volunteers did not significantly change amlodipine systemic exposure. However, strong inhibitors of CYP3A (e.g., itraconazole, clarithromycin) may increase the plasma concentrations of amlodipine to a greater extent [see Drug Interactions (7.1)].

Atorvastatin:

Atorvastatin is a substrate of the hepatic transporters, OATP1B1 and OATP1B3 transporter. Metabolites of atorvastatin are substrates of OATP1B1. Atorvastatin is also identified as a substrate of the efflux transporter BCRP, which may limit the intestinal absorption and biliary clearance of atorvastatin.

Table 6 shows effects of other drugs on the pharmacokinetics of atorvastatin

Table 6. Effect of Co-administered Drugs on the Pharmacokinetics of Atorvastatin

Co-administered drug and dosing regimen | Atorvastatin
 | Dose (mg) | Ratio of AUC& | Ratio of Cmax&
#Cyclosporine 5.2 mg/kg/day, stable dose | 10 mg QDa for 28 days | 8.69 | 10.66
#Tipranavir 500 mg BIDb/ritonavir 200 mg BIDb, 7 days | 10 mg, SDc | 9.36 | 8.58
#Glecaprevir 400 mg QDa/pibrentasvir 120 mg QDa, 7 days | 10 mg QDa for 7 days | 8.28 | 22.00
#Telaprevir 750 mg q8hf, 10 days | 20 mg, SDc | 7.88 | 10.60
#, ‡Saquinavir 400 mg BIDb/ritonavir 400mg BID, 15 days | 40 mg QDa for 4 days | 3.93 | 4.31
#Elbasvir 50 mg QDa/grazoprevir 200 mg QDa, 13 days | 10 mg SDc | 1.95 | 4.34
#Simeprevir 150 mg QDa, 10 days | 40 mg SDc | 2.12 | 1.70
#Clarithromycin 500 mg BIDb, 9 days | 80 mg QDa for 8 days | 4.54 | 5.38
#Darunavir 300 mg BIDb/ritonavir 100 mg BID, 9 days | 10 mg QDa for 4 days | 3.45 | 2.25
#Itraconazole 200 mg QDa, 4 days | 40 mg SDc | 3.32 | 1.20
#Letermovir 480 mg QDa, 10 days | 20 mg SDc | 3.29 | 2.17
#Fosamprenavir 700 mg BIDb/ritonavir 100 mg BIDb, 14 days | 10 mg QDa for 4 days | 2.53 | 2.84
#Fosamprenavir 1400 mg BIDb, 14 days | 10 mg QDa for 4 days | 2.30 | 4.04
#Nelfinavir 1250 mg BIDb, 14 days | 10 mg QDa for 28 days | 1.74 | 2.22
#Grapefruit Juice, 240 mL QDa,* | 40 mg, SDc | 1.37 | 1.16
Diltiazem 240 mg QDa, 28 days | 40 mg, SDc | 1.51 | 1.00
Erythromycin 500 mg QIDe, 7 days | 10 mg, SDc | 1.33 | 1.38
Amlodipine 10 mg, single dose | 80 mg, SDc | 1.18 | 0.91
Cimetidine 300 mg QIDe, 2 weeks | 10 mg QDa for 2 weeks | 1.00 | 0.89
Colestipol 10 g BIDb, 24 weeks | 40 mg QDa for 8 weeks | NA | 0.74**
Maalox TC® 30 mL QDa, 17 days | 10 mg QDa for 15 days | 0.66 | 0.67
Efavirenz 600 mg QDa, 14 days | 10 mg for 3 days | 0.59 | 1.01
#Rifampin 600 mg QDa, 7 days (coadministered) † | 40 mg SDc | 1.12 | 2.90
#Rifampin 600 mg QDa, 5 days (doses separated) † | 40 mg SDc | 0.20 | 0.60
#Gemfibrozil 600 mg BIDb, 7 days | 40 mg SDc | 1.35 | 1.00
#Fenofibrate 160 mg QDa, 7 days | 40 mg SDc | 1.03 | 1.02
Boceprevir 800 mg TIDd, 7 days | 40 mg SDc | 2.32 | 2.66

& Represents ratio of treatments (co-administered drug plus atorvastatin versus atorvastatin alone).

# See Sections 5.1 and 7 for clinical significance.

* Greater increases in AUC (ratio of AUC up to 2.5) and/or Cmax (ratio of Cmax up to 1.71) have been reported with excessive grapefruit consumption (≥ 750 mL to 1.2 liters per day).

** Ratio based on a single sample taken 8 to 16 h post dose.

† Due to the dual interaction mechanism of rifampin, simultaneous co-administration of atorvastatin with rifampin is recommended, as delayed administration of atorvastatin after administration of rifampin has been associated with a significant reduction in atorvastatin plasma concentrations.

‡ The dose of saquinavir plus ritonavir in this study is not the clinically used dose. The increase in atorvastatin exposure when used clinically is likely to be higher than what was observed in this study. Therefore, caution should be applied and the lowest dose necessary should be used.

a Once daily

b Twice daily

c Single dose

d Three times daily

e Four times daily

f Every 8 hours

Effects of Amlodipine besylate and atorvastatin calcium on Other Drugs

Amlodipine:

Amlodipine is a weak inhibitor of CYP3A and may increase exposure to CYP3A substrates.

In vitro data indicate that amlodipine has no effect on the human plasma protein binding of digoxin, phenytoin, warfarin, and indomethacin.

Co-administered amlodipine does not affect the exposure to atorvastatin, digoxin, ethanol and the warfarin prothrombin response time.

Cyclosporine: A prospective study in renal transplant patients (N=11) showed on an average of 40% increase in trough cyclosporine levels when concomitantly treated with amlodipine [see Drug Interactions (7.2)].

Tacrolimus: A prospective study in healthy Chinese volunteers (N=9) with CYP3A5 expressers showed a 2.5-to 4-fold increase in tacrolimus exposure when concomitantly administered with amlodipine compared to tacrolimus alone. This finding was not observed in CYP3A5 non-expressers (N= 6). However, a 3-fold increase in plasma exposure to tacrolimus in a renal transplant patient (CYP3A5 non-expresser) upon initiation of amlodipine for the treatment of post-transplant hypertension resulting in reduction of tacrolimus dose has been reported. Irrespective of the CYP3A5 genotype status, the possibility of an interaction cannot be excluded with these drugs [see Drug Interactions (7.2)].

Atorvastatin:

Table 7 shows the effects of atorvastatin on the pharmacokinetics of other drugs.

Table 7. Effect of Atorvastatin on the Pharmacokinetics of Co-administered Drugs

Atorvastatin | Co-administered drug and dosing regimen
 | Drug/Dose (mg) | Ratio of AUC | Ratio of Cmax
80 mg QDa for 15 days | Antipyrine, 600 mg SDc | 1.03 | 0.89
80 mg QDa for 10 days | #Digoxin 0.25 mg QDa, 20 days | 1.15 | 1.20
40 mg QDa for 22 days | Oral contraceptive QDa, 2 months – norethindrone 1 mg – ethinyl estradiol 35 mcg | 1.281.19 | 1.231.30
10 mg, SD c | Tipranavir 500 mg BIDb/ritonavir 200 mg BIDb, 7 days | 1.08 | 0.96
10 mg QDa for 4 days | Fosamprenavir 1400 mg BIDb, 14 days | 0.73 | 0.82
10 mg QDa for 4 days | Fosamprenavir 700 mg BIDb/ritonavir 100 mg BIDb, 14 days | 0.99 | 0.94

# See Section 7 for clinical significance.

a Once daily

b Twice daily

c Single dose

Atorvastatin had no clinically significant effect on prothrombin time when administered to patients receiving chronic warfarin treatment.

13 NONCLINICAL TOXICOLOGY

13.1 Carcinogenesis, Mutagenesis, Impairment of Fertility

Amlodipine

Rats and mice treated with amlodipine maleate in the diet for up to two years, at concentrations calculated to provide daily dosage levels of 0.5, 1.25, and 2.5 mg amlodipine/kg/day, showed no evidence of a carcinogenic effect of the drug. For the mouse, the highest dose was, on a mg/m^2 basis, similar to the MRHD of 10 mg amlodipine/day.^4 For the rat, the highest dose level was, on a mg/m^2 basis, about twice the MRHD.^4

Mutagenicity studies conducted with amlodipine maleate revealed no drug related effects at either the gene or chromosome levels.

There was no effect on the fertility of rats treated orally with amlodipine maleate (males for 64 days and females for 14 days prior to mating) at doses up to 10 mg amlodipine/kg/day (8 times the MRHD^4 of 10 mg/day on a mg/m^2 basis).

^4 Based on patient weight of 50 kg.

Atorvastatin

In a 2-year carcinogenicity study with atorvastatin calcium in rats at dose levels equivalent to 10, 30, and 100 mg atorvastatin/kg/day, 2 rare tumors were found in muscle in high-dose females: in one, there was a rhabdomyosarcoma and, in another, there was a fibrosarcoma. This dose represents a plasma AUC (0-24) value of approximately 16 times the mean human plasma drug exposure after an 80 mg oral dose.

A 2-year carcinogenicity study in mice given atorvastatin calcium at dose levels equivalent to 100, 200, or 400 mg atorvastatin/kg/day resulted in a significant increase in liver adenomas in high-dose males and liver carcinomas in high-dose females. These findings occurred at plasma AUC (0–24) values of approximately 6 times the mean human plasma drug exposure after an 80 mg oral dose.

In vitro, atorvastatin was not mutagenic or clastogenic in the following tests with and without metabolic activation: the Ames test with Salmonella typhimurium and Escherichia coli, the HGPRT forward mutation assay in Chinese hamster lung cells, and the chromosomal aberration assay in Chinese hamster lung cells. Atorvastatin was negative in the in vivo mouse micronucleus test.

In female rats, atorvastatin at doses up to 225 mg/kg (56 times the human exposure) did not cause adverse effects on fertility. Studies in male rats performed at doses up to 175 mg/kg (15 times the human exposure) produced no changes in fertility. There was aplasia and aspermia in the epididymides of 2 of 10 rats treated with atorvastatin calcium at a dose equivalent to 100 mg atorvastatin/kg/day for 3 months (16 times the human AUC at the 80 mg dose); testis weights were significantly lower at 30 and 100 mg/kg/day and epididymal weight was lower at 100 mg/kg/day. Male rats given the equivalent of 100 mg atorvastatin/kg/day for 11 weeks prior to mating had decreased sperm motility, spermatid head concentration, and increased abnormal sperm. Atorvastatin caused no adverse effects on semen parameters, or reproductive organ histopathology in dogs given doses of atorvastatin calcium equivalent to 10, 40, or 120 mg atorvastatin/kg/day for two years.

14 CLINICAL STUDIES

14.1 Amlodipine for Hypertension

Adult Patients

The antihypertensive efficacy of amlodipine has been demonstrated in a total of 15 double-blind, placebo-controlled, randomized studies involving 800 patients on amlodipine and 538 on placebo. Once daily administration produced statistically significant placebo-corrected reductions in supine and standing blood pressures at 24 hours postdose, averaging about 12/6 mmHg in the standing position and 13/7 mmHg in the supine position in patients with mild to moderate hypertension. Maintenance of the blood pressure effect over the 24-hour dosing interval was observed, with little difference in peak and trough effect. Tolerance was not demonstrated in patients studied for up to 1 year. The 3 parallel, fixed dose, dose response studies showed that the reduction in supine and standing blood pressures was dose related within the recommended dosing range. Effects on diastolic pressure were similar in young and older patients. The effect on systolic pressure was greater in older patients, perhaps because of greater baseline systolic pressure. Effects were similar in black patients and in white patients.

Pediatric Patients

Two hundred sixty-eight hypertensive patients aged 6 to 17 years were randomized first to amlodipine 2.5 or 5 mg once daily for 4 weeks and then randomized again to the same dose or to placebo for another 4 weeks. Patients receiving 2.5 mg or 5 mg at the end of 8 weeks had significantly lower systolic blood pressure than those secondarily randomized to placebo. The magnitude of the treatment effect is difficult to interpret, but it is probably less than 5 mmHg systolic on the 5 mg dose and 3.3 mmHg systolic on the 2.5 mg dose. Adverse events were similar to those seen in adults.

14.2 Amlodipine for Chronic Stable Angina

The effectiveness of 5 to 10 mg/day of amlodipine in exercise-induced angina has been evaluated in 8 placebo-controlled, double-blind clinical trials of up to 6 weeks duration involving 1038 patients (684 amlodipine, 354 placebo) with chronic stable angina. In 5 of the 8 studies, significant increases in exercise time (bicycle or treadmill) were seen with the 10 mg dose. Increases in symptom-limited exercise time averaged 12.8% (63 sec) for amlodipine 10 mg, and averaged 7.9% (38 sec) for amlodipine 5 mg. Amlodipine 10 mg also increased time to 1 mm ST segment deviation in several studies and decreased angina attack rate. The sustained efficacy of amlodipine in angina patients has been demonstrated over long-term dosing. In patients with angina, there were no clinically significant reductions in blood pressures (4/1 mmHg) or changes in heart rate (+0.3 bpm).

14.3 Amlodipine for Vasospastic Angina

In a double-blind, placebo-controlled clinical trial of 4 weeks duration in 50 patients, amlodipine therapy decreased attacks by approximately 4/week compared with a placebo decrease of approximately 1/week (p<0.01). Two of 23 amlodipine and 7 of 27 placebo patients discontinued from the study for lack of clinical improvement.

14.4 Amlodipine for Coronary Artery Disease

In PREVENT, 825 patients with angiographically documented CAD were randomized to amlodipine (5 to 10 mg once daily) or placebo and followed for 3 years. Although the study did not show significance on the primary objective of change in coronary luminal diameter as assessed by quantitative coronary angiography, the data suggested a favorable outcome with respect to fewer hospitalizations for angina and revascularization procedures in patients with CAD.

CAMELOT enrolled 1318 patients with CAD recently documented by angiography, without left main coronary disease and without heart failure or an ejection fraction <40%. Patients (76% males, 89% Caucasian, 93% enrolled at U.S. sites, 89% with a history of angina, 52% without PCI, 4% with PCI and no stent, and 44% with a stent) were randomized to double-blind treatment with either amlodipine (5 to 10 mg once daily) or placebo in addition to standard care that included aspirin (89%), statins (83%), beta-blockers (74%), nitroglycerin (50%), anticoagulants (40%), and diuretics (32%), but excluded other calcium channel blockers. The mean duration of follow-up was 19 months. The primary endpoint was the time to first occurrence of one of the following events: hospitalization for angina pectoris, coronary revascularization, myocardial infarction, cardiovascular death, resuscitated cardiac arrest, hospitalization for heart failure, stroke/TIA, or peripheral vascular disease. A total of 110 (16.6%) and 151 (23.1%) first events occurred in the amlodipine and placebo groups, respectively, for a hazard ratio of 0.691 (95% CI: 0.540– 0.884, p = 0.003). The primary endpoint is summarized in Figure 1 below. The outcome of this study was largely derived from the prevention of hospitalizations for angina and the prevention of revascularization procedures (see Table 8). Effects in various subgroups are shown in Figure 2.

In an angiographic substudy (n=274) conducted within CAMELOT, there was no significant difference between amlodipine and placebo on the change of atheroma volume in the coronary artery as assessed by intravascular ultrasound.

Figure 1. Kaplan-Meier Analysis of Composite Clinical Outcomes for Amlodipine versus Placebo

Figure 2. Effects on Primary Endpoint of Amlodipine versus Placebo across Sub-Groups

Table 8 below summarizes the significant composite endpoint and clinical outcomes from the composites of the primary endpoint. The other components of the primary endpoint including cardiovascular death, resuscitated cardiac arrest, myocardial infarction, hospitalization for heart failure, stroke/TIA, or peripheral vascular disease did not demonstrate a significant difference between amlodipine and placebo.

Table 8. Incidence of Significant Clinical Outcomes for CAMELOT

Clinical Outcomes N (%) | Amlodipine (N=663) | Placebo (N=655) | Risk Reduction (p-value)
Composite CV | 110 | 151 | 31%
Endpoint | (16.6) | (23.1) | (0.003)
Hospitalization for | 51 | 84 | 42%
Angina* | (7.7) | (12.8) | (0.002)
Coronary | 78 | 103 | 27%
Revascularization* | (11.8) | (15.7) | (0.033)

* Total patients with these events.

14.5 Amlodipine for Heart Failure

Amlodipine has been compared to placebo in four 8 to 12 week studies of patients with NYHA Class II/III heart failure, involving a total of 697 patients. In these studies, there was no evidence of worsened heart failure based on measures of exercise tolerance, NYHA classification, symptoms, or left ventricular ejection fraction. In a long-term (follow-up at least 6 months, mean 13.8 months) placebo-controlled mortality/morbidity study of amlodipine 5 to 10 mg in 1153 patients with NYHA Classes III (n=931) or IV (n=222) heart failure on stable doses of diuretics, digoxin, and ACE inhibitors, amlodipine had no effect on the primary endpoint of the study which was the combined endpoint of all-cause mortality and cardiac morbidity (as defined by life-threatening arrhythmia, acute myocardial infarction, or hospitalization for worsened heart failure), or on NYHA classification, or symptoms of heart failure. Total combined all-cause mortality and cardiac morbidity events were 222/571 (39%) for patients on amlodipine and 246/583 (42%) for patients on placebo; the cardiac morbid events represented about 25% of the endpoints in the study.

Another study (PRAISE-2) randomized patients with NYHA Class III (80%) or IV (20%) heart failure without clinical symptoms or objective evidence of underlying ischemic disease, on stable doses of ACE inhibitors (99%), digitalis (99%), and diuretics (99%), to placebo (n=827) or amlodipine (n=827) and followed them for a mean of 33 months. There was no statistically significant difference between amlodipine and placebo in the primary endpoint of all-cause mortality (95% confidence limits from 8% reduction to 29% increase on amlodipine). With amlodipine there were more reports of pulmonary edema.

14.6 Atorvastatin for Prevention of Cardiovascular Disease

In the Anglo-Scandinavian Cardiac Outcomes Trial (ASCOT), the effect of atorvastatin on fatal and non-fatal coronary heart disease was assessed in 10,305 hypertensive patients 40 to 80 years of age (mean of 63 years), without a previous myocardial infarction and with total-C levels ≤251 mg/dL (6.5 mmol/L). Additionally, all patients had at least 3 of the following cardiovascular risk factors: male gender (81.1%), age >55 years (84.5%), smoking (33.2%), diabetes (24.3%), history of CHD in a first-degree relative (26%), TC:HDL >6 (14.3%), peripheral vascular disease (5.1%), left ventricular hypertrophy (14.4%), prior cerebrovascular event (9.8%), specific ECG abnormality (14.3%), proteinuria/albuminuria (62.4%). In this double-blind, placebo-controlled study, patients were treated with anti-hypertensive therapy (Goal BP <140/90 mmHg for non-diabetic patients; <130/80 mm Hg for diabetic patients) and allocated to either atorvastatin 10 mg daily (n=5168) or placebo (n=5137), using a covariate adaptive method that took into account the distribution of nine baseline characteristics of patients already enrolled and minimized the imbalance of those characteristics across the groups. Patients were followed for a median duration of 3.3 years.

The effect of 10 mg/day of atorvastatin on lipid levels was similar to that seen in previous clinical trials.

Atorvastatin significantly reduced the rate of coronary events [either fatal coronary heart disease (46 events in the placebo group vs. 40 events in the atorvastatin group) or non-fatal MI (108 events in the placebo group vs. 60 events in the atorvastatin group)] with a relative risk reduction of 36% [(based on incidences of 1.9% for atorvastatin vs. 3% for placebo), p=0.0005 (see Figure 3)]. The risk reduction was consistent regardless of age, smoking status, obesity, or presence of renal dysfunction. The effect of atorvastatin was seen regardless of baseline LDL levels. Because of the small number of events, results for women were inconclusive.

Figure 3. Effect of Atorvastatin 10 mg/day on Cumulative Incidence of Non-Fatal Myocardial Infarction or Coronary Heart Disease Death (in ASCOT-LLA)

Atorvastatin also significantly decreased the relative risk for revascularization procedures by 42% (incidences of 1.4% for atorvastatin and 2.5% for placebo). Although the reduction of fatal and non-fatal strokes did not reach a pre-defined significance level (p=0.01), a favorable trend was observed with a 26% relative risk reduction (incidences of 1.7% for atorvastatin and 2.3% for placebo). There was no significant difference between the treatment groups for death from cardiovascular causes (p=0.51) or noncardiovascular causes (p=0.17).

In the Collaborative Atorvastatin Diabetes Study (CARDS), the effect of atorvastatin on cardiovascular disease endpoints was assessed in 2838 subjects (94% white, 68% male), ages 40 to 75 with type 2 diabetes based on WHO criteria, without prior history of cardiovascular disease, and with LDL ≤ 160 mg/dL and TG ≤ 600 mg/dL. In addition to diabetes, subjects had 1 or more of the following risk factors: current smoking (23%), hypertension (80%), retinopathy (30%), or microalbuminuria (9%) or macroalbuminuria (3%). No subjects on hemodialysis were enrolled in the study. In this multicenter, placebo-controlled, double-blind clinical trial, subjects were randomly allocated to either atorvastatin 10 mg daily (1,429) or placebo (1,411) in a 1:1 ratio and were followed for a median duration of 3.9 years. The primary endpoint was the occurrence of any of the major cardiovascular events: myocardial infarction, acute CHD death, unstable angina, coronary revascularization, or stroke. The primary analysis was the time to first occurrence of the primary endpoint.

Baseline characteristics of subjects were: mean age of 62 years; mean HbA1c 7.7%; median LDL-C 120 mg/dL; median total-C 207 mg/dL; median TG 151 mg/dL; median HDL-C 52 mg/dL.

The effect of atorvastatin 10 mg/day on lipid levels was similar to that seen in previous clinical trials.

Atorvastatin significantly reduced the rate of major cardiovascular events (primary endpoint events) (83 events in the atorvastatin group vs. 127 events in the placebo group) with a relative risk reduction of 37%, HR 0.63, 95% CI (0.48, 0.83) (p=0.001) (see Figure 4). An effect of atorvastatin was seen regardless of age, sex, or baseline lipid levels.

Atorvastatin significantly reduced the risk of stroke by 48% (21 events in the atorvastatin group vs. 39 events in the placebo group), HR 0.52, 95% CI (0.31, 0.89) (p=0.016) and reduced the risk of MI by 42% (38 events in the atorvastatin group vs. 64 events in the placebo group), HR 0.58, 95.1% CI (0.39, 0.86) (p=0.007). There was no significant difference between the treatment groups for angina, revascularization procedures, and acute CHD death.

There were 61 deaths in the atorvastatin group vs. 82 deaths in the placebo group (HR 0.73, p=0.059).

Figure 4. Effect of Atorvastatin 10 mg/day on Time to Occurrence of Major Cardiovascular Events (myocardial infarction, acute CHD death, unstable angina, coronary revascularization, or stroke) in CARDS

In the Treating to New Targets Study (TNT), the effect of atorvastatin 80 mg/day vs. atorvastatin 10 mg/day on the reduction in cardiovascular events was assessed in 10,001 subjects (94% white, 81% male, 38% ≥65 years) with clinically evident coronary heart disease who had achieved a target LDL-C level <130 mg/dL after completing an 8-week, open-label, run-in period with atorvastatin 10 mg/day. Subjects were randomly assigned to either 10 mg/day or 80 mg/day of atorvastatin and followed for a median duration of 4.9 years. The primary endpoint was the time to first occurrence of any of the following major cardiovascular events (MCVE): death from CHD, non-fatal myocardial infarction, resuscitated cardiac arrest, and fatal and non-fatal stroke. The mean LDL-C, TC, TG, non-HDL, and HDL-C levels at 12 weeks were 73, 145, 128, 98, and 47 mg/dL during treatment with 80 mg of atorvastatin and 99, 177, 152, 129, and 48 mg/dL during treatment with 10 mg of atorvastatin.

Treatment with atorvastatin 80 mg/day significantly reduced the rate of MCVE (434 events in the 80 mg/day group vs. 548 events in the 10 mg/day group) with a relative risk reduction of 22%, HR 0.78, 95% CI (0.69, 0.89), p=0.0002 (see Figure 5 and Table 7). The overall risk reduction was consistent regardless of age (<65, ≥65) or gender.

Figure 5. Effect of Atorvastatin 80 mg/day vs. 10 mg/day on Time to Occurrence of Major Cardiovascular Events (TNT)

Table 9. Overview of Efficacy Results in TNT

Endpoint | Atorvastatin 10 mg (N=5006) |  | Atorvastatin 80 mg (N=4995) |  | HRa (95% CI)
PRIMARY ENDPOINT | n | (%) | n | (%)
First major cardiovascular endpoint | 548 | (10.9) | 434 | (8.7) | 0.78 (0.69, 0.89)
Components of the Primary Endpoint
CHD death | 127 | (2.5) | 101 | (2) | 0.80 (0.61, 1.03)
Non-fatal, non-procedure related MI | 308 | (6.2) | 243 | (4.9) | 0.78 (0.66, 0.93)
Resuscitated cardiac arrest | 26 | (0.5) | 25 | (0.5) | 0.96 (0.56, 1.67)
Stroke (fatal and non-fatal) | 155 | (3.1) | 117 | (2.3) | 0.75 (0.59, 0.96)
SECONDARY ENDPOINTS*
First CHF with hospitalization | 164 | (3.3) | 122 | (2.4) | 0.74 (0.59, 0.94)
First PVD endpoint | 282 | (5.6) | 275 | (5.5) | 0.97 (0.83, 1.15)
First CABG or other coronary revascularization procedureb | 904 | (18.1) | 667 | (13.4) | 0.72 (0.65, 0.80)
First documented angina endpointb | 615 | (12.3) | 545 | (10.9) | 0.88 (0.79, 0.99)
All-cause mortality | 282 | (5.6) | 284 | (5.7) | 1.01 (0.85, 1.19)
Components of All-Cause Mortality
Cardiovascular death | 155 | (3.1) | 126 | (2.5) | 0.81 (0.64, 1.03)
Noncardiovascular death | 127 | (2.5) | 158 | (3.2) | 1.25 (0.99, 1.57)
Cancer death | 75 | (1.5) | 85 | (1.7) | 1.13 (0.83, 1.55)
Other non-CV death | 43 | (0.9) | 58 | (1.2) | 1.35 (0.91, 2)
Suicide, homicide, and other traumatic non-CV death | 9 | (0.2) | 15 | (0.3) | 1.67 (0.73, 3.82)

a Atorvastatin 80 mg: atorvastatin 10 mg

b Component of other secondary endpoints

* Secondary endpoints not included in primary endpoint HR=hazard ratio; CHD=coronary heart disease; CI=confidence interval; MI=myocardial infarction; CHF=congestive heart failure; CV=cardiovascular; PVD=peripheral vascular disease; CABG=coronary artery bypass graft

Confidence intervals for the Secondary Endpoints were not adjusted for multiple comparisons.

Of the events that comprised the primary efficacy endpoint, treatment with atorvastatin 80 mg/day significantly reduced the rate of non-fatal, non-procedure related MI and fatal and non-fatal stroke, but not CHD death or resuscitated cardiac arrest (Table 7). Of the predefined secondary endpoints, treatment with atorvastatin 80 mg/day significantly reduced the rate of coronary revascularization, angina, and hospitalization for heart failure, but not peripheral vascular disease. The reduction in the rate of CHF with hospitalization was only observed in the 8% of patients with a prior history of CHF.

There was no significant difference between the treatment groups for all-cause mortality (Table 7). The proportions of subjects who experienced cardiovascular death, including the components of CHD death and fatal stroke, were numerically smaller in the atorvastatin 80 mg group than in the atorvastatin 10 mg treatment group. The proportions of subjects who experienced noncardiovascular death were numerically larger in the atorvastatin 80 mg group than in the atorvastatin 10 mg treatment group.

In the Incremental Decrease in Endpoints Through Aggressive Lipid Lowering Study (IDEAL), treatment with atorvastatin 80 mg/day was compared to treatment with simvastatin 20 to 40 mg/day in 8,888 subjects up to 80 years of age with a history of CHD to assess whether reduction in CV risk could be achieved. Patients were mainly male (81%), white (99%) with an average age of 61.7 years, and an average LDL-C of 121.5 mg/dL at randomization; 76% were on statin therapy. In this prospective, randomized, open-label, blinded endpoint (PROBE) trial with no run-in period, subjects were followed for a median duration of 4.8 years. The mean LDL-C, TC, TG, HDL, and non-HDL-C levels at Week 12 were 78, 145, 115, 45, and 100 mg/dL during treatment with 80 mg of atorvastatin and 105, 179, 142, 47, and 132 mg/dL during treatment with 20 to 40 mg of simvastatin.

There was no significant difference between the treatment groups for the primary endpoint, the rate of first major coronary event (fatal CHD, non-fatal MI, and resuscitated cardiac arrest): 411 (9.3%) in the atorvastatin 80 mg/day group vs. 463 (10.4%) in the simvastatin 20 to 40 mg/day group, HR 0.89, 95% CI (0.78, 1.01), p=0.07.

There were no significant differences between the treatment groups for all-cause mortality: 366 (8.2%) in the atorvastatin 80 mg/day group vs. 374 (8.4%) in the simvastatin 20 to 40 mg/day group. The proportions of subjects who experienced CV or non-CV death were similar for the atorvastatin 80 mg group and the simvastatin 20 to 40 mg group.

14.7 Atorvastatin for Hyperlipidemia and Mixed Dyslipidemia

Atorvastatin reduces total-C, LDL-C, very-low density lipoprotein cholesterol (VLDL-C), apo B, and TG, and increases HDL-C in patients with hyperlipidemia (heterozygous familial and nonfamilial) and mixed dyslipidemia (Fredrickson Types IIa and IIb). Therapeutic response is seen within 2 weeks, and maximum response is usually achieved within 4 weeks and maintained during chronic therapy.

Atorvastatin is effective in a wide variety of patient populations with hyperlipidemia, with and without hypertriglyceridemia, in men and women, and in the elderly.

In two multicenter, placebo-controlled, dose-response studies in patients with hyperlipidemia, atorvastatin given as a single dose over 6 weeks significantly reduced total-C, LDL-C, apo B, and TG. (Pooled results are provided in Table 10.)

Table 10. Dose Response in Patients with Primary Hyperlipidemia (Adjusted Mean % Change From Baseline)a

Dose | N | TC | LDL-C | Apo B | TG | HDL-C | Non-HDL- C/HDL-C
Placebo | 21 | 4 | 4 | 3 | 10 | -3 | 7
10 | 22 | -29 | -39 | -32 | -19 | 6 | -34
20 | 20 | -33 | -43 | -35 | -26 | 9 | -41
40 | 21 | -37 | -50 | -42 | -29 | 6 | -45
80 | 23 | -45 | -60 | -50 | -37 | 5 | -53

a Results are pooled from 2 dose-response studies.

In patients with Fredrickson Types IIa and IIb hyperlipoproteinemia pooled from 24 controlled trials, the median (25th and 75th percentile) percent changes from baseline in HDL-C for atorvastatin 10, 20, 40, and 80 mg were 6.4 (-1.4, 14), 8.7 (0, 17), 7.8 (0, 16), and 5.1 (-2.7, 15), respectively. Additionally, analysis of the pooled data demonstrated consistent and significant decreases in total-C, LDL-C, TG, total-C/HDL-C, and LDL-C/HDL-C.

In three multicenter, double-blind studies in patients with hyperlipidemia, atorvastatin was compared to other statins. After randomization, patients were treated for 16 weeks with either atorvastatin 10 mg per day or a fixed dose of the comparative agent (Table 11).

Table 11. Mean Percentage Change from Baseline at Endpoint (Double-Blind, Randomized, Active-Controlled Trials)

Treatment (Daily Dose) | N | Total-C | LDL-C | Apo B | TG | HDL-C | Non-HDL-C/ HDL-C
Study 1
Atorvastatin 10 mg | 707 | -27a | -36a | -28a | -17a | +7 | -37a
Lovastatin 20 mg 95% CI for Diff^1 | 191 | -19 -9.2, -6.5 | -27 -10.7, -7.1 | -20 -10, -6.5 | -6 -15.2, -7.1 | +7 -1.7, 2 | -28 -11.1, -7.1
Study 2 Atorvastatin 10 mg | 222 | -25b | -35b | -27b | -17b | +6 | -36b
Pravastatin 20 mg 95% CI for Diff^1 | 77 | -17 -10.8, -6.1 | -23 -14.5, -8.2 | -17 -13.4, -7.4 | -9 -14.1, -0.7 | +8 -4.9, 1.6 | -28 -11.5, -4.1
Study 3
Atorvastatin 10 mg | 132 | -29c | -37c | -34c | -23c | +7 | -39c
Simvastatin 10 mg 95% CI for Diff^1 | 45 | -24 -8.7, -2.7 | -30 -10.1, -2.6 | -30 -8, -1.1 | -15 -15.1, -0.7 | +7 -4.3, 3.9 | -33 -9.6, -1.9

^1 A negative value for the 95% CI for the difference between treatments favors atorvastatin for all except HDL-C, for which a positive value favors atorvastatin. If the range does not include 0, this indicates a statistically significant difference.

a Significantly different from lovastatin, ANCOVA, p ≤0.05

b Significantly different from pravastatin, ANCOVA, p ≤0.05

c Significantly different from simvastatin, ANCOVA, p ≤0.05

The impact on clinical outcomes of the differences in lipid-altering effects between treatments shown in Table 11 is not known. Table 11 does not contain data comparing the effects of atorvastatin 10 mg and higher doses of lovastatin, pravastatin, and simvastatin. The drugs compared in the studies summarized in the table are not necessarily interchangeable.

14.8 Atorvastatin for Hypertriglyceridemia

The response to atorvastatin in 64 patients with isolated hypertriglyceridemia (Fredrickson Type IV) treated across several clinical trials is shown in the table below (Table 12). For the atorvastatin-treated patients, median (min, max) baseline TG level was 565 (267–1502).

Table 12. Combined Patients with Isolated Elevated TG: Median (min, max) Percentage Change From Baseline

 | Placebo (N=12) | Atorvastatin 10 mg (N=37) | Atorvastatin 20 mg (N=13) | Atorvastatin 80 mg (N=14)
TG | -12.4 (-36.6, 82.7) | -41 (-76.2, 49.4) | -38.7 (-62.7, 29.5) | -51.8 (-82.8, 41.3)
Total-C | -2.3 (-15.5, 24.4) | -28.2 (-44.9, -6.8) | -34.9 (-49.6, -15.2) | -44.4 (-63.5, -3.8)
LDL-C | 3.6 (-31.3, 31.6) | -26.5 (-57.7, 9.8) | -30.4 (-53.9, 0.3) | -40.5 (-60.6, -13.8)
HDL-C | 3.8 (-18.6, 13.4) | 13.8 (-9.7, 61.5) | 11 (-3.2, 25.2) | 7.5 (-10.8, 37.2)
VLDL-C | -1 (-31.9, 53.2) | -48.8 (-85.8, 57.3) | -44.6 (-62.2, -10.8) | -62 (-88.2, 37.6)
non-HDL-C | -2.8 (-17.6, 30) | -33 (-52.1, -13.3) | -42.7 (-53.7, -17.4) | -51.5 (-72.9, -4.3)

14.9 Atorvastatin for Dysbetalipoproteinemia

The results of an open-label crossover study of 16 patients (genotypes: 14 apo E2/E2 and 2 apo E3/E2) with dysbetalipoproteinemia (Fredrickson Type III) are shown in the table below (Table 13).

Table 13. Open-Label Crossover Study of 16 Patients with Dysbetalipoproteinemia (Fredrickson Type III)

 |  | Median % Change (min, max)
Median (min, max) at |  | Atorvastatin | Atorvastatin
Baseline (mg/dL) |  | 10 mg | 80 mg
Total-C | 442 (225, 1320) | -37 (-85, 17) | -58 (-90, -31)
TG | 678 (273, 5990) | -39 (-92, -8) | -53 (-95, -30)
Intermediate-density lipoprotein cholesterol (IDL-C) + VLDL-C | 215 (111, 613) | -32 (-76, 9) | -63 (-90, -8)
non-HDL-C | 411 (218, 1272) | -43 (-87, -19) | -64 (-92, -36)

14.10 Atorvastatin for Homozygous Familial Hypercholesterolemia

In a study without a concurrent control group, 29 patients ages 6 years to 37 years with HoFH received maximum daily doses of 20 to 80 mg of atorvastatin. The mean LDL-C reduction in this study was 18%. Twenty-five patients with a reduction in LDL-C had a mean response of 20% (range of 7% to 53%, median of 24%); the remaining 4 patients had 7% to 24% increases in LDL-C. Five of the 29 patients had absent LDL-receptor function. Of these, 2 patients also had a portacaval shunt and had no significant reduction in LDL-C. The remaining 3 receptor-negative patients had a mean LDL-C reduction of 22%.

14.11 Atorvastatin for Heterozygous Familial Hypercholesterolemia in Pediatric Patients

In a double-blind, placebo-controlled study followed by an open-label phase, 187 boys and post-menarchal girls 10 years to 17 years of age (mean age 14.1 years) with HeFH or severe hypercholesterolemia, were randomized to atorvastatin (n=140) or placebo (n=47) for 26 weeks and then all received atorvastatin for 26 weeks. Inclusion in the study required 1) a baseline LDL-C level ≥ 190 mg/dL or 2) a baseline LDL-C level ≥ 160 mg/dL and positive family history of FH or documented premature cardiovascular disease in a first or second-degree relative. The mean baseline LDL-C value was 218.6 mg/dL (range: 138.5 to 385 mg/dL) in the atorvastatin group compared to 230 mg/dL (range: 160 to 324.5 mg/dL) in the placebo group. The dosage of atorvastatin (once daily) was 10 mg for the first 4 weeks and uptitrated to 20 mg if the LDL-C level was > 130 mg/dL. The number of atorvastatin-treated patients who required uptitration to 20 mg after Week 4 during the double-blind phase was 78 (55.7%).

Atorvastatin significantly decreased plasma levels of total-C, LDL-C, TG, and apolipoprotein B during the 26-week double-blind phase (see Table 14).

Table 14. Lipid-Altering Effects of Atorvastatin in Adolescent Boys and Girls with Heterozygous Familial Hypercholesterolemia or Severe Hypercholesterolemia (Mean Percentage Change from Baseline at Endpoint in Intention-to-Treat Population)

DOSAGE | N | Total-C | LDL-C | HDL-C | TG | Apo B
Placebo | 47 | -1.5 | -0.4 | -1.9 | 1 | 0.7
Atorvastatin | 140 | -31.4 | -39.6 | 2.8 | -12 | -34

The mean achieved LDL-C value was 130.7 mg/dL (range: 70 to 242 mg/dL) in the atorvastatin group compared to 228.5 mg/dL (range: 152 to 385 mg/dL) in the placebo group during the 26-week double-blind phase.

Atorvastatin was also studied in a three year open-label, uncontrolled trial that included 163 patients with HeFH who were 10 years to 15 years old (82 boys and 81 girls). All patients had a clinical diagnosis of HeFH confirmed by genetic analysis (if not already confirmed by family history). Approximately 98% were Caucasian, and less than 1% were Black or Asian. Mean LDL-C at baseline was 232 mg/dL. The starting atorvastatin dosage was 10 mg once daily and doses were adjusted to achieve a target of <130 mg/dL LDL-C. The reductions in LDL-C from baseline were generally consistent across age groups within the trial as well as with previous clinical studies in both adult and pediatric placebo-controlled trials.

14.12 Amlodipine besylate and atorvastatin calcium for Hypertension and Dyslipidemia

In a double-blind, placebo-controlled study, a total of 1660 patients with co-morbid hypertension and dyslipidemia received once daily treatment with eight dose combinations of amlodipine and atorvastatin (5/10, 10/10, 5/20, 10/20, 5/40, 10/40, 5/80, or 10/80 mg), amlodipine alone (5 mg or 10 mg), atorvastatin alone (10 mg, 20 mg, 40 mg, or 80 mg), or placebo. In addition to concomitant hypertension and dyslipidemia, 15% of the patients had diabetes mellitus, 22% were smokers, and 14% had a positive family history of cardiovascular disease. At eight weeks, all eight combination-treatment groups of amlodipine and atorvastatin demonstrated statistically significant dose-related reductions in systolic blood pressure (SBP), diastolic blood pressure (DBP), and LDL-C compared to placebo, with no overall modification of effect of either component on SBP, DBP, and LDL-C (Table 15).

Table 15. Effects of Amlodipine and Atorvastatin on Blood Pressure and LDL-C

BP (mmHg) | Atorvastatin
Amlodipine | 0 mg | 10 mg | 20 mg | 40 mg | 80 mg
0 mg | — -9.8/-4.3 | -1.5/-0.8 | -3.2/-0.6 | -3.2/-1.8 | -3.4/-0.8
5 mg | — -9.8/-4.3 | -10.7/-4.9 | -12.3/-6.1 | -9.7/-4 | -9.2/-5.1
10 mg | -13.2/-7.1 | -12.9/-5.8 | -13.1/-7.3 | -13.3/-6.5 | -14.6/-7.8
LDL-C (% change) | Atorvastatin
Amlodipine | 0 mg | 10 mg | 20 mg | 40 mg | 80 mg
0 mg | — 1 | -32.3 | -38.4 | -42 | -46.1
5 mg | — 1 | -37.6 | -41.2 | -43.8 | -47.3
10 mg | -1.4 | -35.5 | -37.5 | -42.1 | -48

16 HOW SUPPLIED/STORAGE AND HANDLING

Amlodipine besylate and atorvastatin calcium tablets contain amlodipine besylate USP and atorvastatin calcium equivalent to amlodipine and atorvastatin in the dose strengths described below.

Amlodipine besylate and atorvastatin calcium tablets 2.5 mg/10 mg are white to off-white, round, film coated tablets debossed ‘R’ on one side and ‘407’ on other side and are supplied in bottles of 30’s, 60’s, 90’s and 500’s.

Bottles of 30 NDC 43598-323-30

Bottles of 60 NDC 43598-323-60

Bottles of 90 NDC 43598-323-90

Bottles of 500 NDC 43598-323-05

Amlodipine besylate and atorvastatin calcium tablets 2.5 mg/20 mg are white to off-white, round, film coated tablets debossed ‘R’ on one side and ‘408’ on other side and are supplied in bottles of 30’s, 60’s, 90’s and 500’s.

Bottles of 30 NDC 43598-320-30

Bottles of 60 NDC 43598-320-60

Bottles of 90 NDC 43598-320-90

Bottles of 500 NDC 43598-320-05

Amlodipine besylate and atorvastatin calcium tablets 2.5 mg/40 mg are white to off-white, round, film coated tablets debossed ‘R’ on one side and ‘409’ on other side and are supplied in bottles of 30’s, 60’s, 90’s and 500’s.

Bottles of 30 NDC 43598-317-30

Bottles of 60 NDC 43598-317-60

Bottles of 90 NDC 43598-317-90

Bottles of 500 NDC 43598-317-05

Amlodipine besylate and atorvastatin calcium tablets 5 mg/10 mg are white to off-white, oval shaped, film coated tablets debossed ‘R’ on one side and ‘410’ on other side and are supplied in bottles of 30’s, 60’s, 90’s and 500’s.

Bottles of 30 NDC 43598-322-30

Bottles of 60 NDC 43598-322-60

Bottles of 90 NDC 43598-322-90

Bottles of 500 NDC 43598-322-05

Amlodipine besylate and atorvastatin calcium tablets 5 mg/20 mg are white to off-white, oval shaped, film coated tablets debossed ‘R’ on one side and ‘411’ on other side and are supplied in bottles of 30’s, 60’s, 90’s and 500’s.

Bottles of 30 NDC 43598-319-30

Bottles of 60 NDC 43598-319-60

Bottles of 90 NDC 43598-319-90

Bottles of 500 NDC 43598-319-05

Amlodipine besylate and atorvastatin calcium tablets 5 mg/40 mg are white to off-white, oval shaped, film coated tablets debossed ‘R’ on one side and ‘412’ on other side and are supplied in bottles of 30’s, 60’s, 90’s and 500’s.

Bottles of 30 NDC 43598-316-30

Bottles of 60 NDC 43598-316-60

Bottles of 90 NDC 43598-316-90

Bottles of 500 NDC 43598-316-05

Amlodipine besylate and atorvastatin calcium tablets 5 mg/80 mg are white to off-white, oval shaped, film coated tablets debossed ‘R’ on one side and ‘413’ on other side and are supplied in bottles of 30’s, 60’s, 90’s and 500’s.

Bottles of 30 NDC 43598-314-30

Bottles of 60 NDC 43598-314-60

Bottles of 90 NDC 43598-314-90

Bottles of 500 NDC 43598-314-05

Amlodipine besylate and atorvastatin calcium tablets 10 mg/10 mg are blue, oval shaped, film coated tablets debossed ‘R’ on one side and ‘414’ on other side and are supplied in bottles of 30’s, 60’s, 90’s and 500’s.

Bottles of 30 NDC 43598-321-30

Bottles of 60 NDC 43598-321-60

Bottles of 90 NDC 43598-321-90

Bottles of 500 NDC 43598-321-05

Amlodipine besylate and atorvastatin calcium tablets 10 mg/20 mg are blue, oval shaped, film coated tablets debossed ‘R’ on one side and ‘415’ on other side and are supplied in bottles of 30’s, 60’s, 90’s and 500’s.

Bottles of 30 NDC 43598-318-30

Bottles of 60 NDC 43598-318-60

Bottles of 90 NDC 43598-318-90

Bottles of 500 NDC 43598-318-05

Amlodipine besylate and atorvastatin calcium tablets 10 mg/40 mg are blue, oval shaped, film coated tablets debossed ‘R’ on one side and ‘416’ on other side and are supplied in bottles of 30’s, 60’s, 90’s and 500’s.

Bottles of 30 NDC 43598-315-30

Bottles of 60 NDC 43598-315-60

Bottles of 90 NDC 43598-315-90

Bottles of 500 NDC 43598-315-05

Amlodipine besylate and atorvastatin calcium tablets 10 mg/80 mg are blue, oval shaped, film coated tablets debossed ‘R’ on one side and ‘417’ on other side and are supplied in bottles of 30’s, 60’s, 90’s and 500’s.

Bottles of 30 NDC 43598-313-30

Bottles of 60 NDC 43598-313-60

Bottles of 90 NDC 43598-313-90

Bottles of 500 NDC 43598-313-05

Store Amlodipine besylate and atorvastatin calcium tablets at 20°C to 25°C (68°F to 77°F) [See USP Controlled Room Temperature].

17 PATIENT COUNSELING INFORMATION

Advise the patient to read the FDA-approved patient labeling (Patient Information).

Information for Patients

Because of the risk of myopathy with statins, the drug class to which atorvastatin belongs, advise patients to report unexplained muscle pain, tenderness, or weakness, particularly if accompanied by malaise or fever.

Advise patients taking atorvastatin that cholesterol is a chronic condition and they should adhere to their medication along with their National Cholesterol Education Program (NCEP)-recommended diet, a regular exercise program as appropriate, and periodic testing of a fasting lipid panel to determine goal attainment.

Advise patients about substances they should not take concomitantly with atorvastatin [see Warnings and Precautions (5.1)]. Patients should inform other healthcare professionals prescribing a new medication that they are taking amlodipine besylate and atorvastatin calcium.

Muscle Pain: Advise patients starting therapy with amlodipine besylate and atorvastatin calcium of the risk of myopathy and to report promptly any unexplained muscle pain, tenderness, or weakness particularly if accompanied by malaise or fever or if these muscle signs or symptoms persist after discontinuing amlodipine besylate and atorvastatin calcium. The risk of this occurring is increased when taking certain types of medication or consuming larger quantities (>1 liter) of grapefruit juice. They should discuss all medication, both prescription and over the counter, with their healthcare professional.

Liver Enzymes: Advise patients treated with amlodipine besylate and atorvastatin calcium to report promptly any symptoms that may indicate liver injury, including fatigue, anorexia, right upper abdominal discomfort, dark urine, or jaundice.

Embryofetal Toxicity: Advise females of reproductive potential of the risk to a fetus, to use effective contraception during treatment and to inform their healthcare provider of a known or suspected pregnancy while using amlodipine besylate and atorvastatin calcium [see Contraindications (4) and Use in Specific Populations (8.1, 8.3)].

Lactation: Advise women not to breastfeed during treatment with amlodipine besylate and atorvastatin calcium [see Contraindications (4) and Use in Specific Populations (8.2)].

PATIENT INFORMATION

AMLODIPINE BESYLATE AND ATORVASTATIN CALCIUM TABLETS

(am loe’di peen bes’ i late and a tor” va stat’ in kal’ see um)

(from 2.5mg/10mg to 10mg/80mg tablets)

Read the patient information that comes with amlodipine besylate and atorvastatin calcium tablets before you start taking it, and each time you get a refill. There may be new information. This information does not replace talking with your doctor about your condition or treatment. If you have any questions about amlodipine besylate and atorvastatin calcium tablets, ask your doctor or pharmacist.

What are amlodipine besylate and atorvastatin calcium tablets?

Amlodipine besylate and atorvastatin calcium tablets are a prescription drug that combines amlodipine besylate and atorvastatin calcium in one pill.

Amlodipine besylate and atorvastatin calcium tablets are used in adults who need both amlodipine besylate and atorvastatin calcium.

Amlodipine besylate tablets are used to treat:

- High blood pressure (hypertension) and
- Chest pain (angina) and
- Blocked arteries of the heart (coronary artery disease)

Atorvastatin calcium tablets are used to lower the levels of “bad” cholesterol and triglycerides in your blood. It can also raise the levels of “good” cholesterol.

Atorvastatin calcium tablets are also used to lower the risk for heart attack, stroke, certain types of heart surgery, and chest pain in patients who have heart disease or risk factors for heart disease such as:

- age, smoking, high blood pressure, low levels of “good” cholesterol, heart disease in the family.

Atorvastatin calcium tablets can lower the risk for heart attack or stroke in patients with diabetes and risk factors such as:

- diabetic eye or kidney problems, smoking, or high blood pressure.

Amlodipine besylate and atorvastatin calcium tablets has not been studied in children.

Who should not use amlodipine besylate and atorvastatin calcium tablets?

Do not use amlodipine besylate and atorvastatin calcium tablets if you:

- Are pregnant or think you may be pregnant, or are planning to become pregnant. Amlodipine besylate and atorvastatin calcium tablets may harm your unborn baby. If you get pregnant, stop taking amlodipine besylate and atorvastatin calcium tablets and call your doctor right away.
- Are breastfeeding. Amlodipine besylate and atorvastatin calcium tablets can pass into your breast milk and may harm your baby. Do not breastfeed if you take amlodipine besylate and atorvastatin calcium tablets.
- Have liver problems.
- Are allergic to anything in amlodipine besylate and atorvastatin calcium tablets. The active ingredients are atorvastatin calcium and amlodipine besylate. See the end of this leaflet for a complete list of ingredients.

What should I tell my doctor before taking amlodipine besylate and atorvastatin calcium tablets?

Tell your doctor about all of your health conditions, including, if you have:

- heart disease
- muscle aches or weakness
- diabetes
- thyroid problems
- kidney problems
- or drink more than 2 glasses of alcohol daily

Tell your doctor about all the medicines you take including prescription and nonprescription medicines, vitamins, and herbal supplements. Amlodipine besylate and atorvastatin calcium tablets and some other medicines can interact, causing serious side effects. Especially tell your doctor if you take medicines for:

Tell your doctor about all the medicines you take including prescription and nonprescription medicines, vitamins, and herbal supplements. Amlodipine besylate and atorvastatin calcium tablets and some other medicines can interact, causing serious side effects. Especially tell your doctor if you take medicines for:

- your immune system
- birth control
- infections
- heart failure
- cholesterol
- HIV (AIDS)
- hepatitis C virus
- anti-virals

You can use nitroglycerin and amlodipine besylate and atorvastatin calcium tablets together. If you take nitroglycerin for chest pain (angina), do not stop taking it while taking amlodipine besylate and atorvastatin calcium tablets.

Know all the medicines you take. Keep a list of them with you to show your doctor and pharmacist.

How should I take amlodipine besylate and atorvastatin calcium tablets?

- Take amlodipine besylate and atorvastatin calcium tablets once a day, exactly as your doctor tells you. Do not change your dose or stop amlodipine besylate and atorvastatin calcium tablets without talking to your doctor.
- Take amlodipine besylate and atorvastatin calcium tablets each day at any time of day, at about the same time each day. Amlodipine besylate and atorvastatin calcium tablets can be taken with or without food.
- Do not break the tablets before taking them. Talk to your doctor if you have a problem swallowing pills.
- Your doctor should start you on a low-fat diet before giving you amlodipine besylate and atorvastatin calcium tablets. Stay on this low-fat diet when you take amlodipine besylate and atorvastatin calcium tablets.
- If you miss a dose, take it as soon as you remember. Do not take amlodipine besylate and atorvastatin calcium tablets if it has been more than 12 hours since your missed dose. Just take the next dose at your regular time. Do not take 2 doses of amlodipine besylate and atorvastatin calcium tablets at the same time.
- If too much amlodipine besylate and atorvastatin calcium tablets are taken by accident, call your doctor or poison control center, or go to the nearest emergency room.

What should I avoid while taking amlodipine besylate and atorvastatin calcium tablets?

- Avoid getting pregnant. If you get pregnant, stop taking amlodipine besylate and atorvastatin calcium tablets right away and call your doctor.
- Do not breastfeed. Amlodipine besylate and atorvastatin calcium tablets can pass into your breast milk and may harm your baby.

What are possible side effects of amlodipine besylate and atorvastatin calcium tablets?

Amlodipine besylate and atorvastatin calcium tablets can cause serious side effects. These side effects happen only to a small number of people. Your doctor can monitor you for them. These side effects usually go away if your dose is lowered or amlodipine besylate and atorvastatin calcium tablets are stopped. These serious side effects include:

- Muscle problems. Amlodipine besylate and atorvastatin calcium tablets can cause serious muscle problems that can lead to kidney problems, including kidney failure. You have a higher chance for muscle problems if you are taking certain other medicines with amlodipine besylate and atorvastatin calcium tablets.
- Liver problems. Your doctor should do blood tests to check your liver before you start taking amlodipine besylate and atorvastatin calcium tablets and if you have symptoms of liver problems while you take amlodipine besylate and atorvastatin calcium tablets. Call your doctor right away if you have the following symptoms of liver problems:
- feel tired or weak
- loss of appetite
- upper belly pain
- dark amber colored urine
- yellowing of your skin or the whites of your eyes
- Low blood pressure or dizziness
- Muscle rigidity, tremor and/or abnormal muscle movement

Call your doctor right away if:

- you have muscle problems like weakness, tenderness, or pain that happen without a good reason, especially if you also have a fever or feel more tired than usual. This may be an early sign of a rare muscle problem.
- muscle problems that do not go away even after your doctor has advised you to stop taking amlodipine besylate and atorvastatin calcium tablets. Your doctor may do further tests to diagnose the cause of your muscle problems.
- allergic reactions including swelling of the face, lips, tongue, and/or throat that may cause difficulty in breathing or swallowing which may require treatment right away
- you have nausea and vomiting, stomach pain
- you are passing brown or dark-colored urine
- you feel more tired than usual
- your skin and white of your eyes get yellow
- you have allergic skin reactions
- Chest pain that does not go away or gets worse. Sometimes when you start amlodipine besylate and atorvastatin calcium tablets or increase your dose, chest pain can get worse or a heart attack can happen. If this happens, call your doctor or go to the emergency room right away.

Common side effects of amlodipine besylate and atorvastatin calcium tablets include:

- Diarrhea
- Swelling of your legs or ankles
- Nausea
- Upset stomach
- Muscle and joint pain
- Alterations in some laboratory blood tests

Additional side effects have been reported: tiredness, tendon problems, memory loss, and confusion.

Talk to your doctor or pharmacist about side effects that bother you or do not go away. There are other side effects of amlodipine besylate and atorvastatin calcium tablets. Ask your doctor or pharmacist for a complete list.

How do I store amlodipine besylate and atorvastatin calcium tablets?

- Store amlodipine besylate and atorvastatin calcium tablets at room temperature, 20° to 25°C (68° to 77°F)
- Do not keep medicine that is out-of-date or that you no longer need.
- Keep amlodipine besylate and atorvastatin calcium tablets and all medicines out of the reach of children. Keep medicines in places where children cannot get it.

General information about amlodipine besylate and atorvastatin calcium tablets

Medicines are sometimes prescribed for conditions that are not mentioned in patient information leaflets. Do not use amlodipine besylate and atorvastatin calcium tablets for a condition for which it was not prescribed. Do not give amlodipine besylate and atorvastatin calcium tablets to other people, even if they have the same problem you have. It may harm them.

This leaflet summarizes the most important information about amlodipine besylate and atorvastatin calcium tablets. If you want more information, talk with your doctor. Ask your doctor or pharmacist for information about amlodipine besylate and atorvastatin calcium tablets written for health professionals or call 1-888-375-3784.

What is high blood pressure (hypertension)?

You have high blood pressure when the force of blood against the walls of your arteries stays high. This can damage your heart and other parts of your body. Drugs that lower blood pressure lower your risk of having a stroke or heart attack.

What is angina (chest pain)?

Angina is a pain that keeps coming back when part of your heart does not get enough blood. It feels like something is pressing or squeezing your chest under the breastbone. Sometimes you can feel it in your shoulders, arms, neck, jaw, or back.

What is cholesterol?

Cholesterol is a fat-like substance made in your body. It is also found in foods. You need some cholesterol for good health, but too much is not good for you. Cholesterol can clog your blood vessels.

What is a heart attack?

A heart attack occurs when heart muscle does not get enough blood. Symptoms include chest pain, trouble breathing, nausea, and weakness. Heart muscle cells may be damaged or die. The heart cannot pump well or may stop beating.

What is a stroke?

A stroke occurs when nerve cells in the brain do not get enough blood. The cells may be damaged or die. The damaged cells may cause weakness or problems speaking or thinking.

What are the ingredients in amlodipine besylate and atorvastatin calcium tablets?

Active ingredients: amlodipine besylate USP, atorvastatin calcium

Inactive ingredients: colloidal silicon dioxide, crospovidone, hydroxy propyl cellulose, magnesium stearate, microcrystalline cellulose, pregelatinized starch, sodium bicarbonate, sodium lauryl sulfate

Film coating: Opadry- II White 85G18490 (Polyethylene glycol, polyvinyl alcohol, lecithin, talc and titanium dioxide), or Opadry- II Blue 85G50642 (FD&C Blue No.2, polyethylene glycol, polyvinyl alcohol, lecithin, talc and titanium dioxide).

Rx only

Manufactured by

Dr. Reddy’s Laboratories Limited

Bachupally – 500 090 INDIA

Revised: 0221

Dispense with Patient Information Sheet available at:

www.drreddys.com/pi/amloandatorvastatintabs.pdf

PACKAGE LABEL PRINCIPAL DISPLAY PANEL SECTION

Amlodipine besylate and Atorvastatin calcium Tablets, 2.5/10 mg- Container Label

Unvarnished Area Consists of: 2D Barcode, Lot Number, Expiry Date and Serial Number

PACKAGE LABEL

Amlodipine besylate and Atorvastatin calcium Tablets, 2.5/20 mg- Container Label

Unvarnished Area Consists of: 2D Barcode, Lot Number, Expiry Date and Serial Number

PACKAGE LABEL

Amlodipine besylate and Atorvastatin calcium Tablets, 2.5/40 mg- Container Label

Unvarnished Area Consists of: 2D Barcode, Lot Number, Expiry Date and Serial Number

PACKAGE LABEL

Amlodipine besylate and Atorvastatin calcium Tablets, 5/10 mg- Container Label

Unvarnished Area Consists of: 2D Barcode, Lot Number, Expiry Date and Serial Number

PACKAGE LABEL

Amlodipine besylate and Atorvastatin calcium Tablets, 5/20 mg- Container Label

Unvarnished Area Consists of: 2D Barcode, Lot Number, Expiry Date and Serial Number

PACKAGE LABEL

Amlodipine besylate and Atorvastatin calcium Tablets, 5/40 mg- Container Label

Unvarnished Area Consists of: 2D Barcode, Lot Number, Expiry Date and Serial Number

PACKAGE LABEL

Amlodipine besylate and Atorvastatin calcium Tablets, 5/80 mg- Container Label

Unvarnished Area Consists of: 2D Barcode, Lot Number, Expiry Date and Serial Number

PACKAGE LABEL

Amlodipine besylate and Atorvastatin calcium Tablets, 10/10 mg- Container Label

Unvarnished Area Consists of: 2D Barcode, Lot Number, Expiry Date and Serial Number

PACKAGE LABEL

Amlodipine besylate and Atorvastatin calcium Tablets, 10/20 mg- Container Label

Unvarnished Area Consists of: 2D Barcode, Lot Number, Expiry Date and Serial Number

PACKAGE LABEL

Amlodipine besylate and Atorvastatin calcium Tablets, 10/40 mg- Container Label

Unvarnished Area Consists of: 2D Barcode, Lot Number, Expiry Date and Serial Number

PACKAGE LABEL

Amlodipine besylate and Atorvastatin calcium Tablets, 10/80 mg- Container Label

Unvarnished Area Consists of: 2D Barcode, Lot Number, Expiry Date and Serial Number